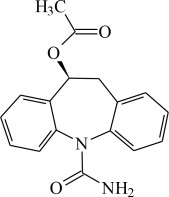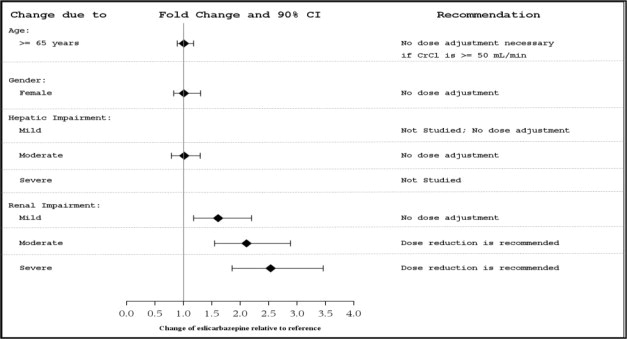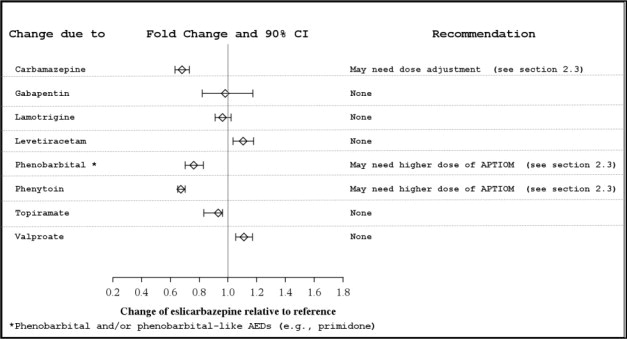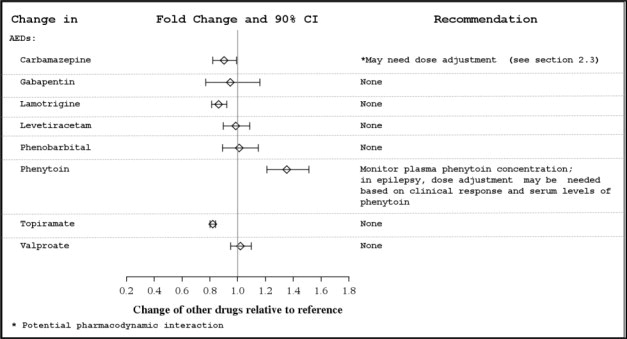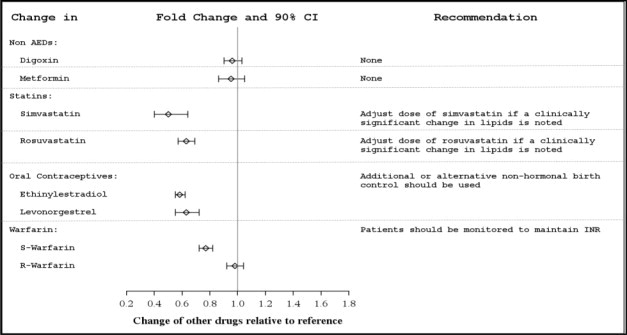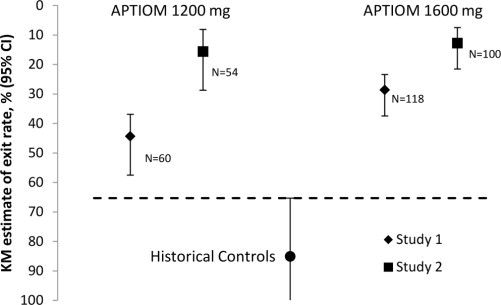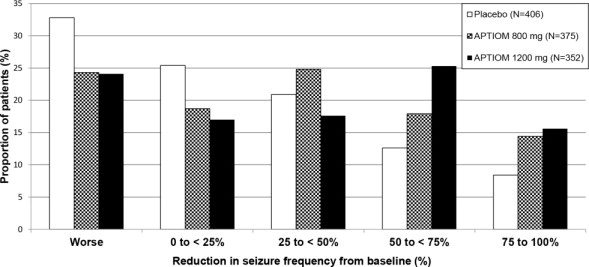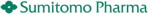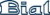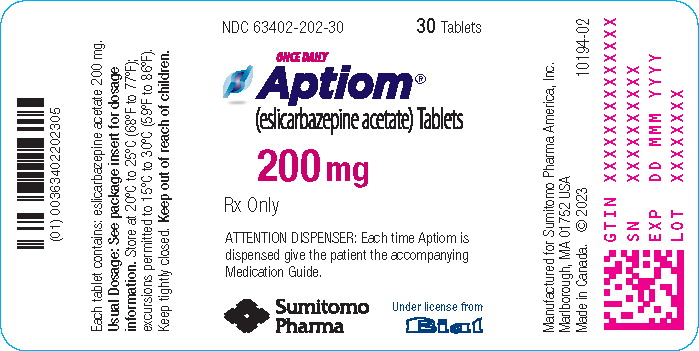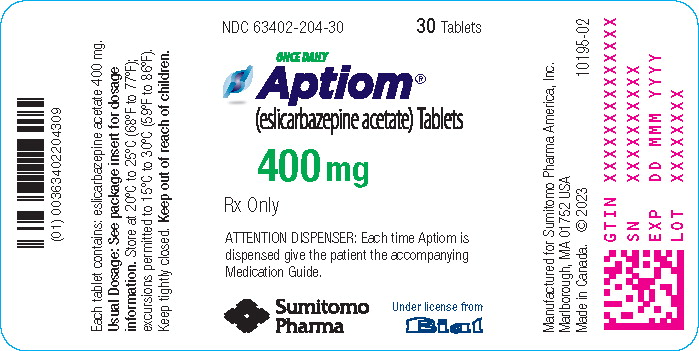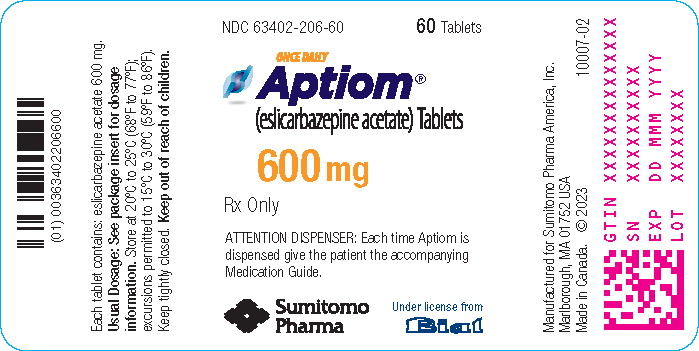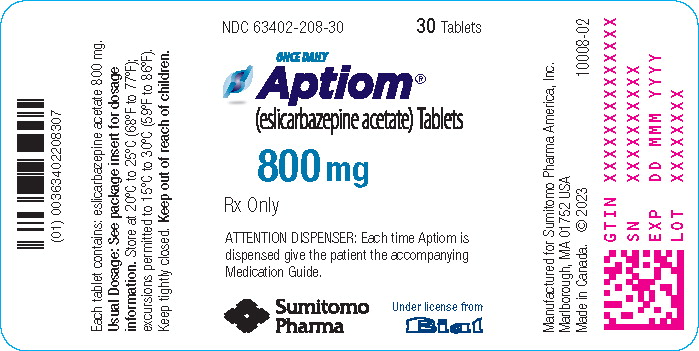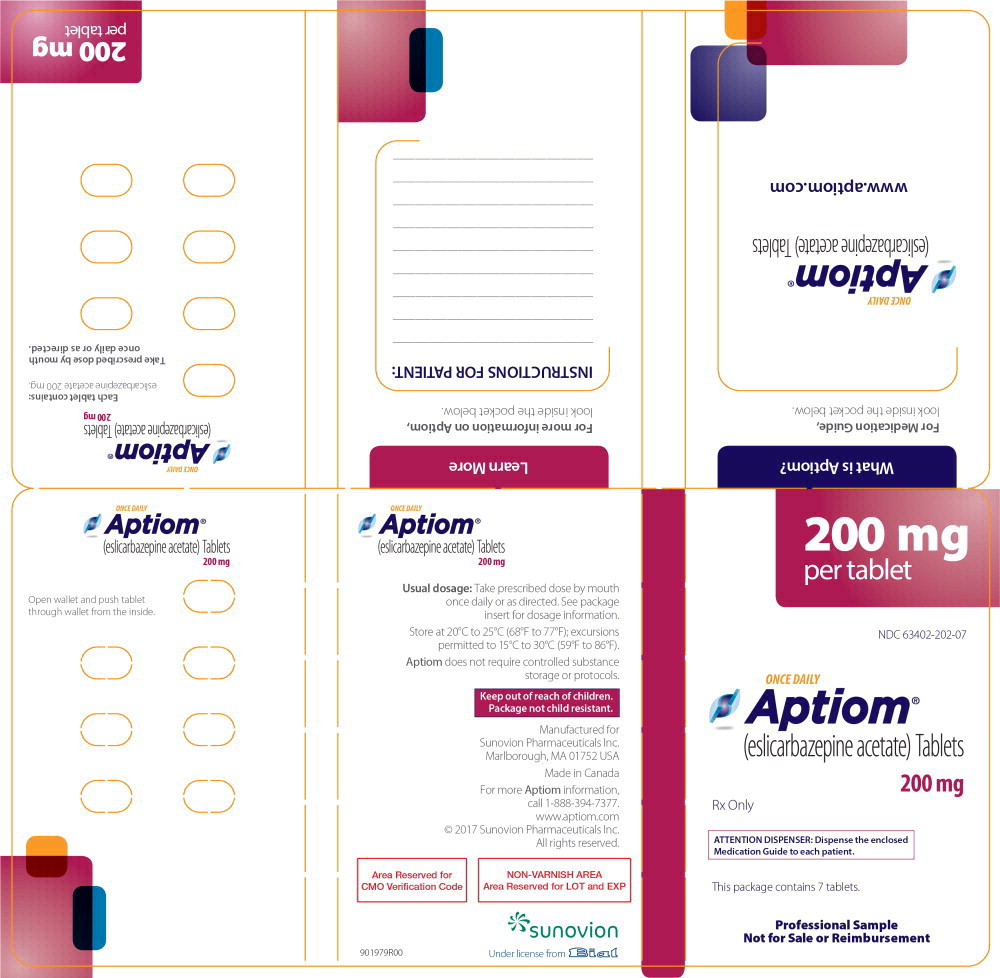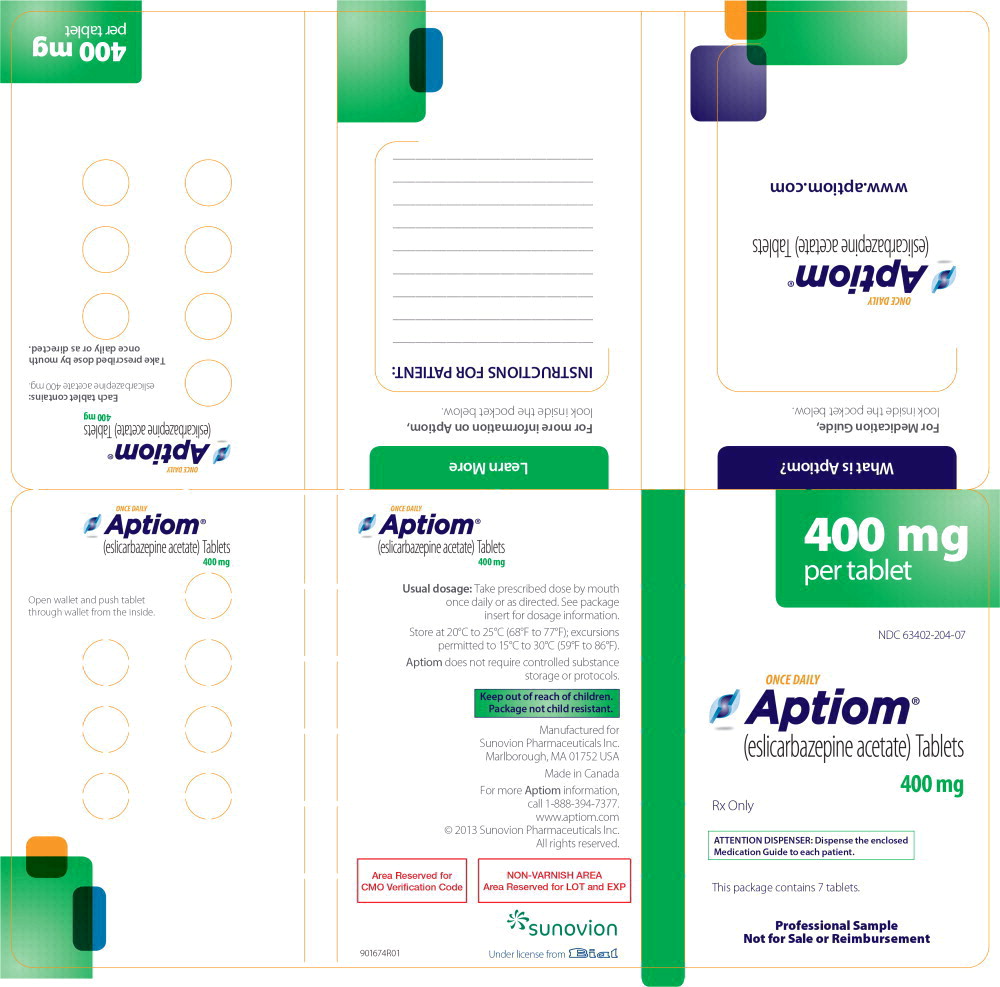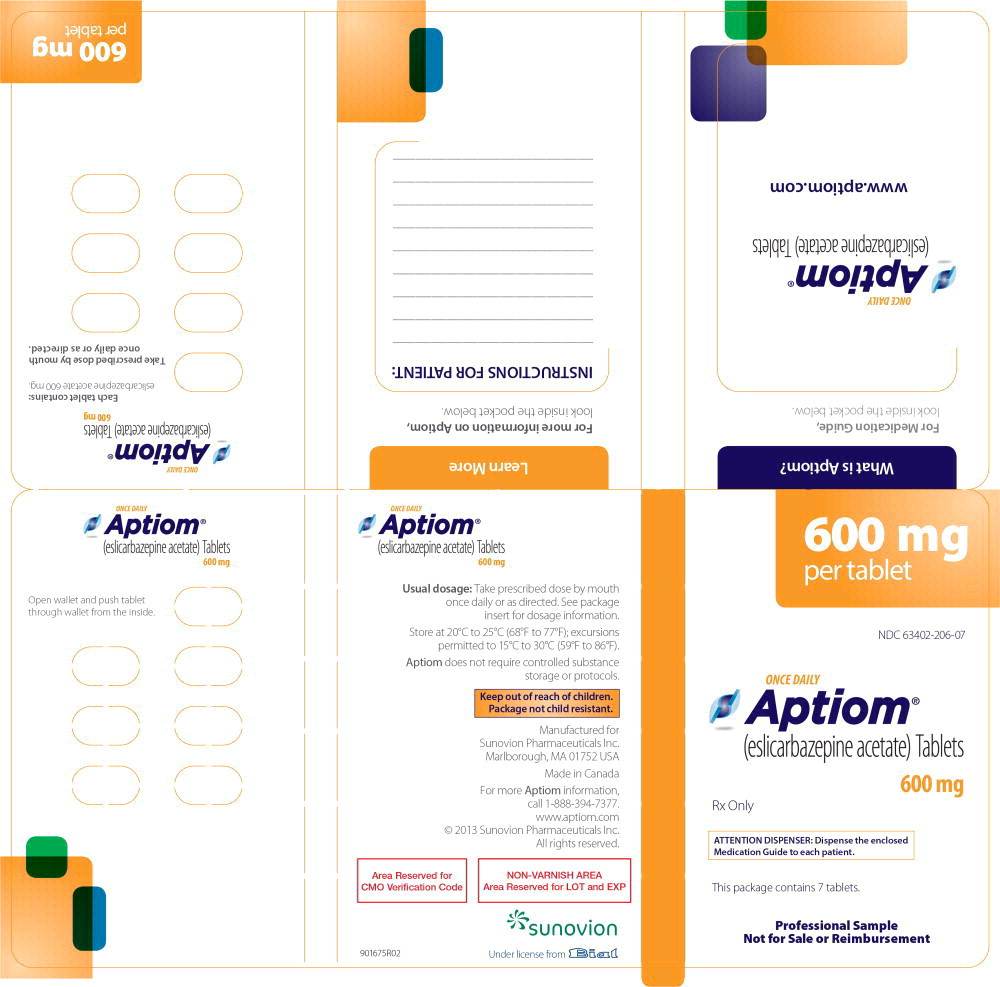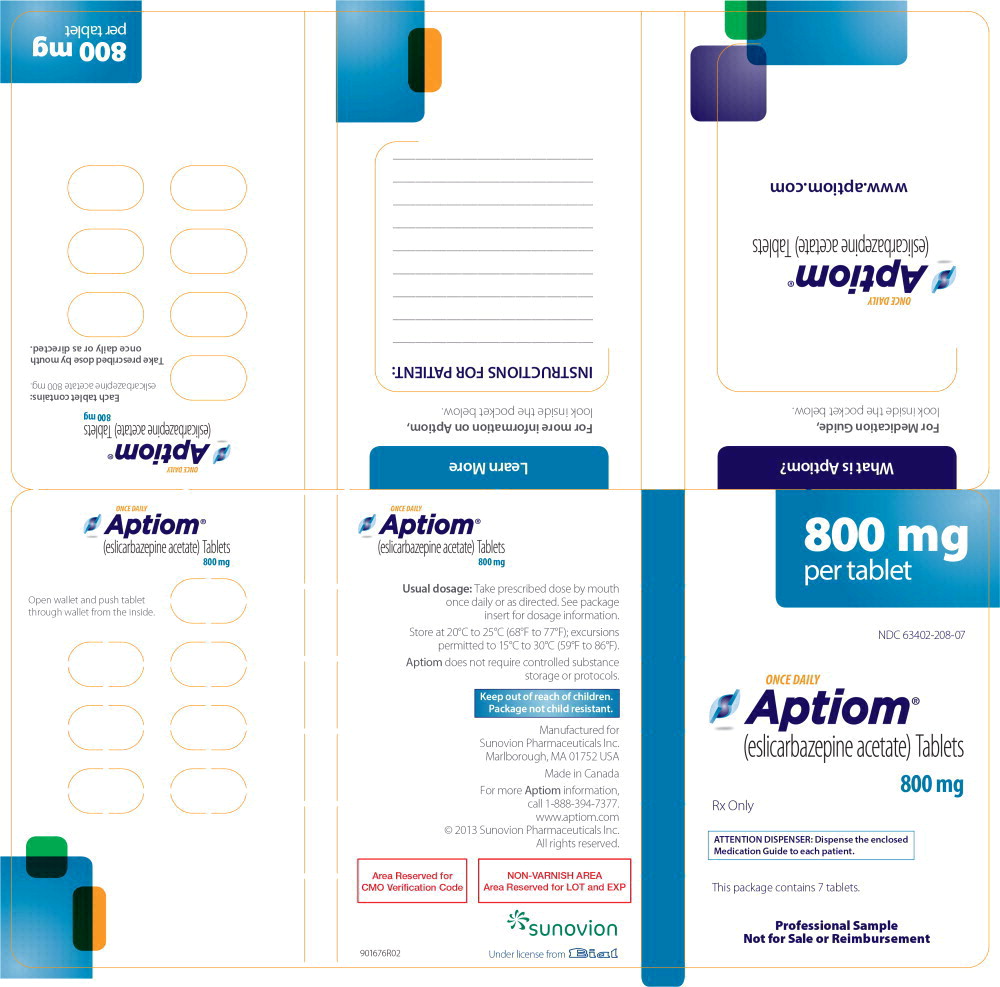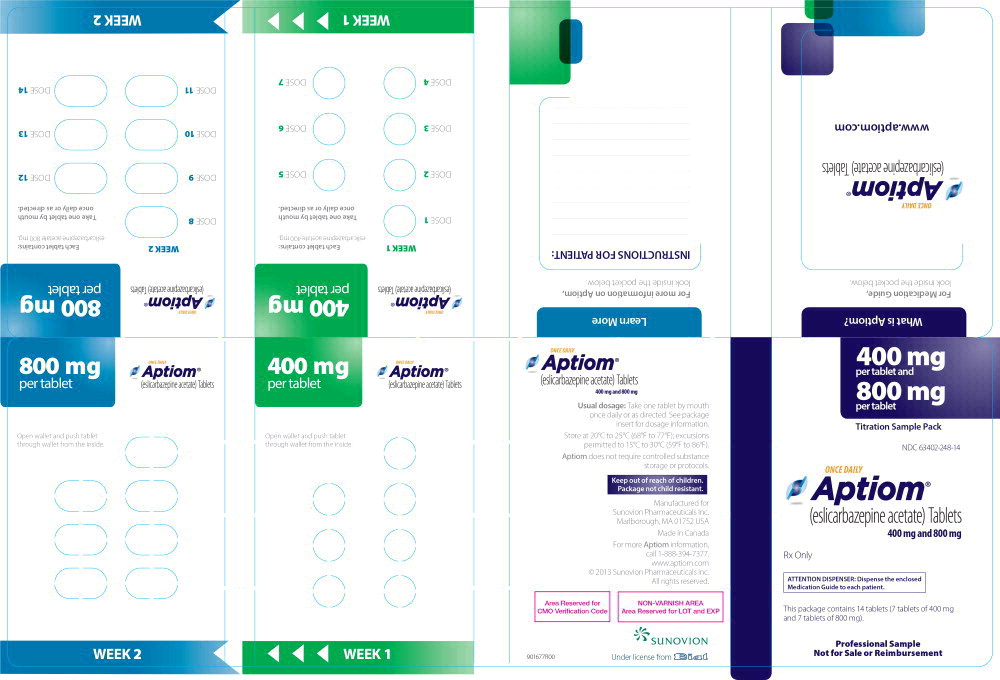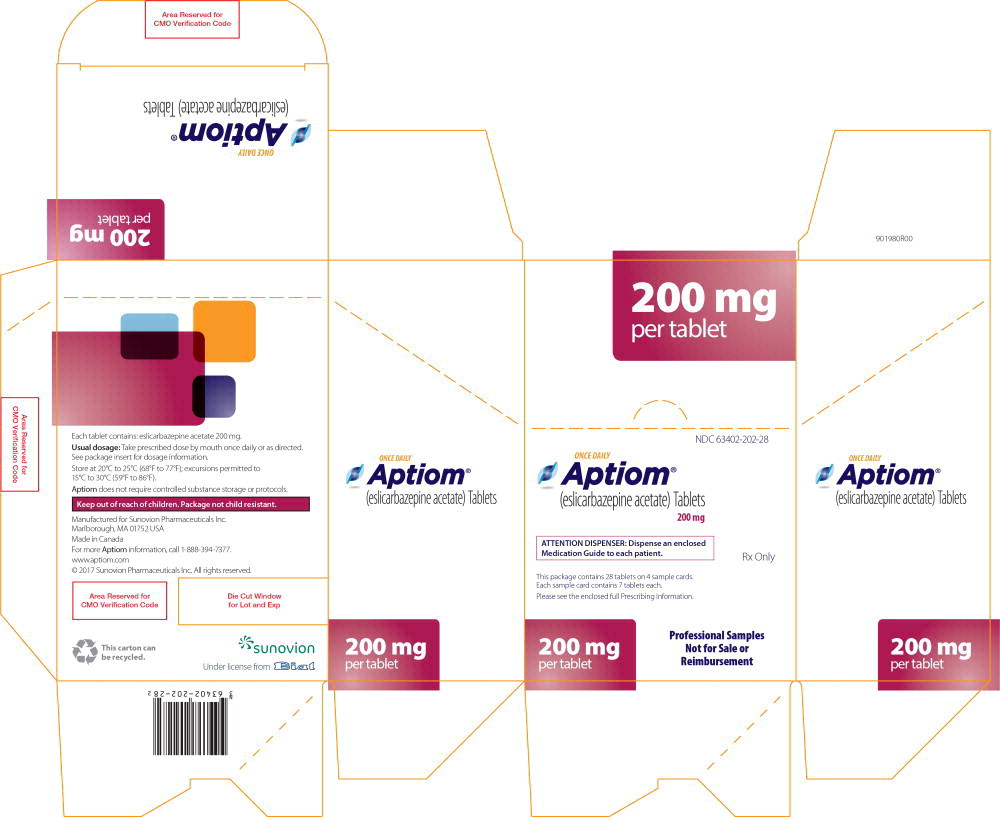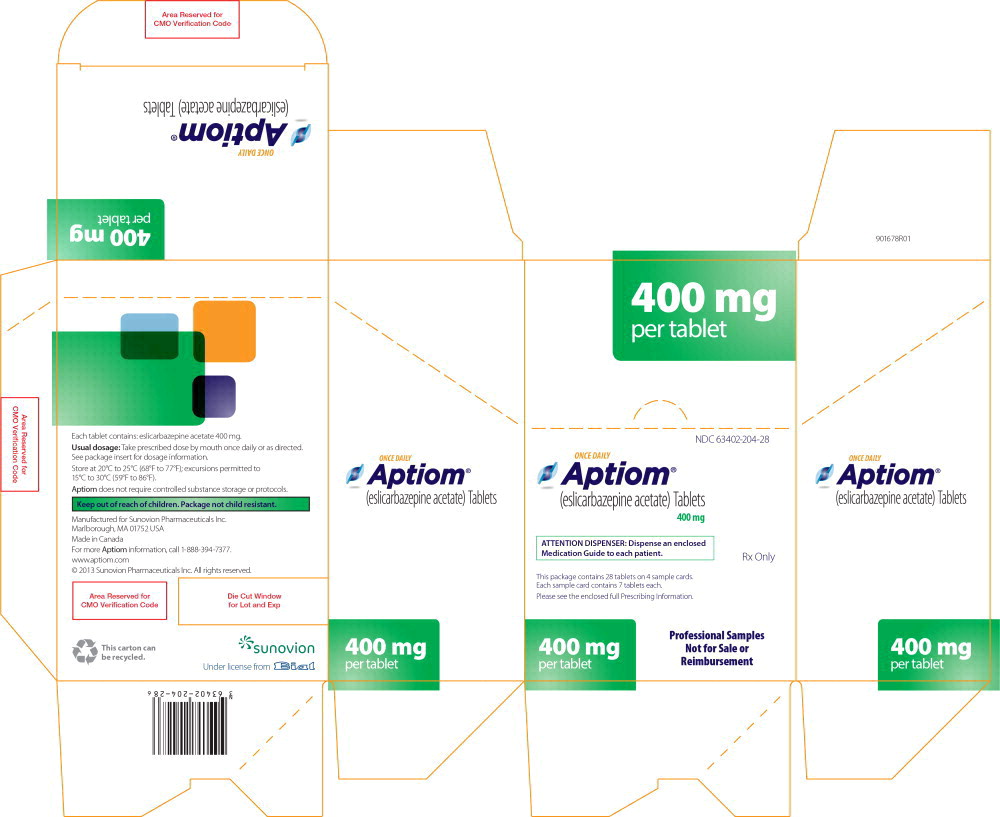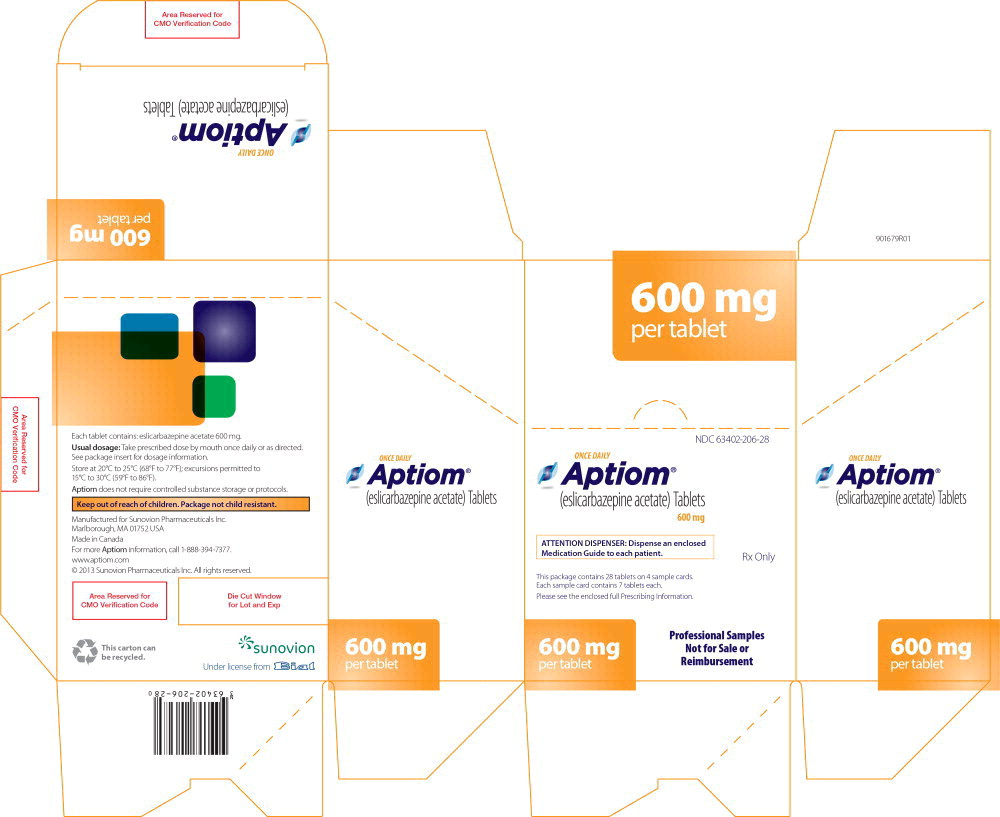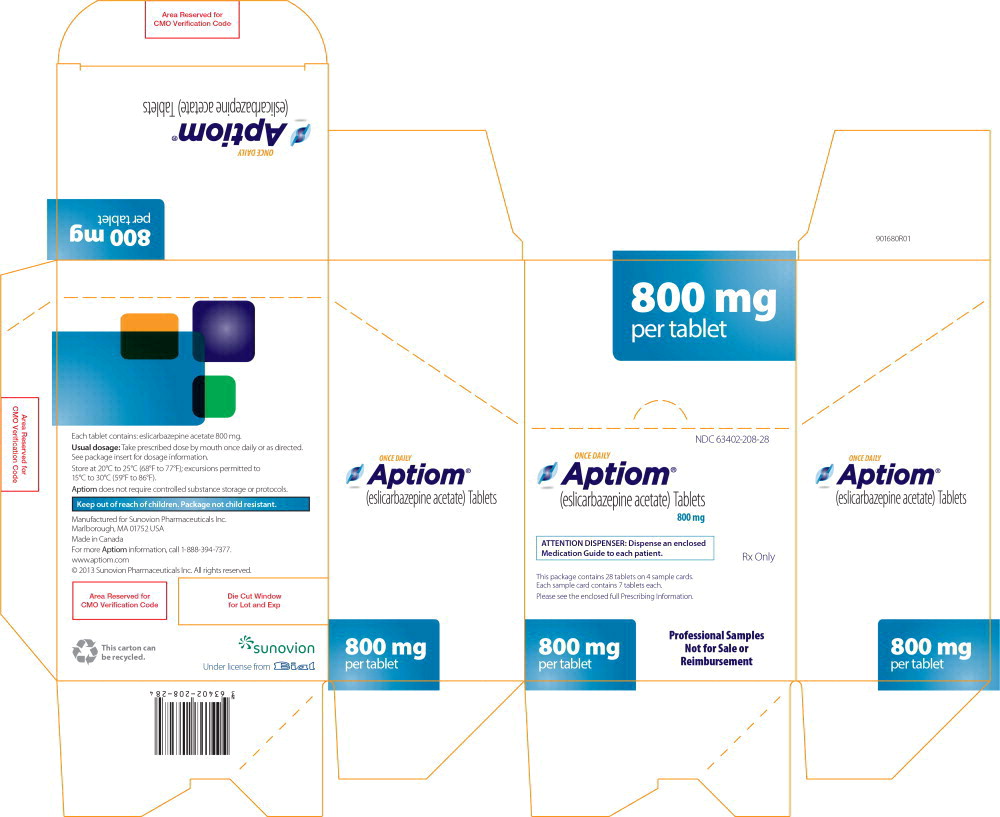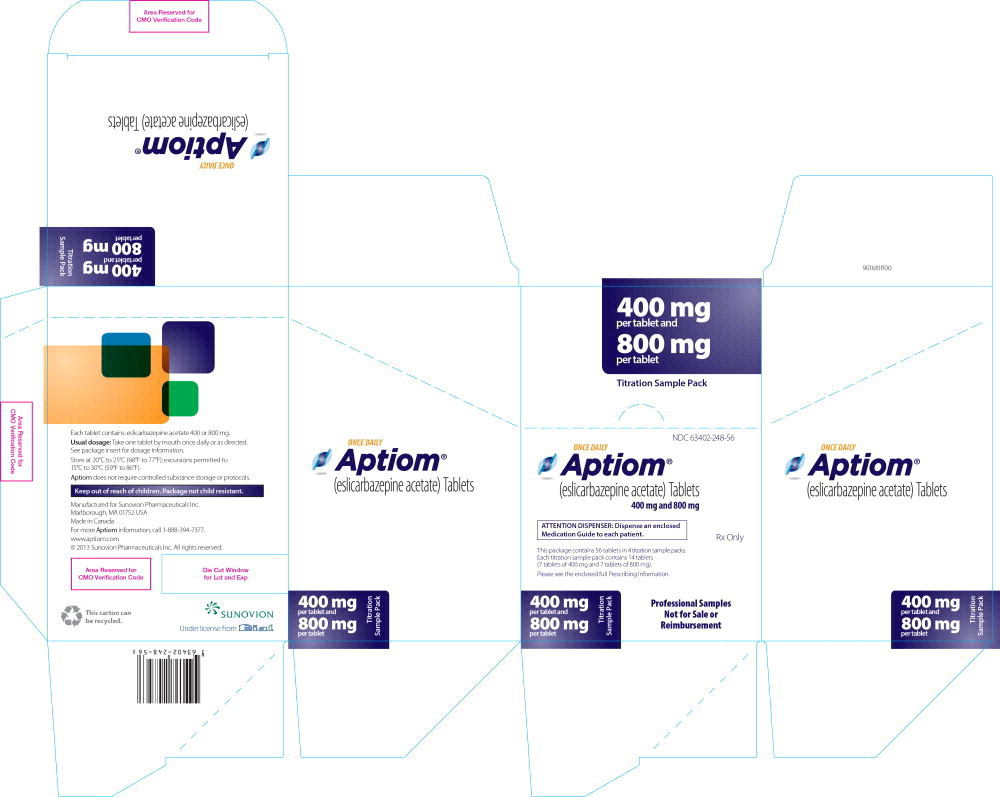 DRUG LABEL: Aptiom
NDC: 63402-202 | Form: TABLET
Manufacturer: Sumitomo Pharma America, Inc.
Category: prescription | Type: HUMAN PRESCRIPTION DRUG LABEL
Date: 20231110

ACTIVE INGREDIENTS: ESLICARBAZEPINE ACETATE 200 mg/1 1
INACTIVE INGREDIENTS: POVIDONE K30; CROSCARMELLOSE SODIUM; MAGNESIUM STEARATE

HIGHLIGHTS OF PRESCRIBING INFORMATION

These highlights do not include all the information needed to use APTIOM safely and effectively. See full prescribing information for APTIOM.
APTIOM® (eslicarbazepine acetate) tablets, for oral use
Initial U.S. Approval: 2013

1 INDICATIONS AND USAGE

APTIOM is indicated for the treatment of partial-onset seizures in patients 4 years of age and older. (1)

2 DOSAGE AND ADMINISTRATION

- Adult Patients: The recommended initial dosage of APTIOM is 400 mg once daily. For some patients, treatment may be initiated at 800 mg once daily if the need for seizure reduction outweighs an increased risk of adverse reactions. Increase the dose in weekly increments of 400 mg to 600 mg once daily, based on clinical response and tolerability, to a recommended maintenance dosage of 800 mg to 1600 mg once daily. (2.2)
- Pediatric Patients: The recommended dosage of APTIOM is based on body weight and is administered orally once daily. Increase the dose in weekly intervals based on clinical response and tolerability, to the recommended maintenance dosage. (2.2)
- Patients with Moderate or Severe Renal Impairment: Reduce dosage by 50%. (2.4)

3 DOSAGE FORMS AND STRENGTHS

Tablets: 200 mg, 400 mg, 600 mg, 800 mg (3)

4 CONTRAINDICATIONS

Hypersensitivity to eslicarbazepine acetate or oxcarbazepine. (4)

5 WARNINGS AND PRECAUTIONS

- Suicidal Behavior and Ideation: Monitor for suicidal thoughts or behavior. (5.1)
- Serious Dermatologic Reactions, Drug Reaction with Eosinophilia and Systemic Symptoms (DRESS), Anaphylactic Reactions and Angioedema: Monitor and discontinue if another cause cannot be established. (5.2, 5.3, 5.4)
- Hyponatremia: Monitor sodium levels in patients at risk or patients experiencing hyponatremia symptoms. (5.5)
- Neurological Adverse Reactions: Monitor for dizziness, disturbance in gait and coordination, somnolence, fatigue, cognitive dysfunction, and visual changes. Use caution when driving or operating machinery. (5.6)
- Withdrawal of APTIOM: Withdraw APTIOM gradually to minimize the risk of increased seizure frequency and status epilepticus. (2.6, 5.7, 8.1)
- Drug Induced Liver Injury: Discontinue APTIOM in patients with jaundice or evidence of significant liver injury. (5.8)
- Hematologic Adverse Reactions: Consider discontinuing. (5.10)

6 ADVERSE REACTIONS

- Most common adverse reactions in adult patients receiving APTIOM (≥4% and ≥2% greater than placebo): dizziness, somnolence, nausea, headache, diplopia, vomiting, fatigue, vertigo, ataxia, blurred vision, and tremor. (6.1)
- Adverse reactions in pediatric patients are similar to those seen in adult patients.

To report SUSPECTED ADVERSE REACTIONS, contact Sumitomo Pharma America, Inc. at 1-877-737-7226 or FDA at 1-800-FDA-1088 or www.fda.gov/medwatch.

7 DRUG INTERACTIONS

- Carbamazepine: May need dose adjustment for APTIOM or carbamazepine. (2.3, 5.6, 7.1)
- Phenytoin: Higher dosage of APTIOM may be necessary and dose adjustment may be needed for phenytoin. (2.3, 7.1, 7.2)
- Phenobarbital or Primidone: Higher dosage of APTIOM may be necessary. (2.3, 7.1)
- Hormonal Contraceptives: APTIOM may decrease the effectiveness of hormonal contraceptives. (7.4, 8.3)

8 USE IN SPECIFIC POPULATIONS

Pregnancy: Based on animal data, may cause fetal harm. (8.1)

FULL PRESCRIBING INFORMATION

1 INDICATIONS AND USAGE

APTIOM is indicated for the treatment of partial-onset seizures in patients 4 years of age and older.

2 DOSAGE AND ADMINISTRATION

2.1 Important Administration Instructions

Instruct patients to administer APTIOM either as whole or as crushed tablets. Instruct patients to take APTIOM either with or without food. The APTIOM dosing regimen depends on age, weight, and renal function.

2.2 General Dosing Recommendations

Monotherapy and Adjunctive Therapy

Adult Patients

The recommended initial dosage of APTIOM is 400 mg administered orally once daily. For some patients, treatment may be initiated at 800 mg once daily if the need for seizure reduction outweighs an increased risk of adverse reactions during initiation [see Adverse Reactions (6.1)]. Dosage should be increased in weekly increments of 400 mg to 600 mg, based on clinical response and tolerability, to a recommended maintenance dosage of 800 mg to 1600 mg once daily. For patients on APTIOM monotherapy, the 800 mg once daily maintenance dose should generally be considered in patients who are unable to tolerate a 1200 mg daily dose. For patients on APTIOM adjunctive therapy, the 1600 mg daily dose should generally be considered in patients who did not achieve a satisfactory response with a 1200 mg daily dose.

Pediatric Patients (4 to 17 Years of Age)

In pediatric patients 4 to 17 years of age, the recommended dosing regimen is dependent upon body weight and is administered orally once daily. The recommended initial dosage of APTIOM is shown in Table 1. Dosage should be increased based on clinical response and tolerability, no more frequently than once per week. Titration increments should not exceed those shown in Table 1. The daily maintenance dosage should not exceed the maintenance dosage for each body weight range shown in Table 1.

Table 1: APTIOM Once Daily Dosage Schedule for Pediatric Patients 4 to 17 Years of Age
Body Weight Range | Initial and Maximum Titration Increment Dosage (mg/day) | Maintenance Dosage (mg/day)
11 to 21 kg | 200 | 400 to 600
22 to 31 kg | 300 | 500 to 800
32 to 38 kg | 300 | 600 to 900
more than 38 kg | 400 | 800 to 1200

2.3 Dosage Modifications with Other Antiepileptic Drugs

Some adverse reactions occur more frequently when patients take APTIOM adjunctively with carbamazepine [see Warnings and Precautions (5.6)]. However, carbamazepine reduces the plasma concentration of eslicarbazepine [see Drug Interactions (7.1)]. When APTIOM and carbamazepine are taken concomitantly, the dose of APTIOM or carbamazepine may need to be adjusted based on efficacy and tolerability. For patients taking other enzyme-inducing AEDs (i.e., phenobarbital, phenytoin, and primidone), higher doses of APTIOM may be needed [see Drug Interactions (7.1)].

APTIOM should not be taken as an adjunctive therapy with oxcarbazepine.

2.4 Dosage Modifications in Patients with Renal Impairment

In patients with moderate and severe renal impairment (i.e., creatinine clearance < 50 mL/min), the initial, titration, and maintenance dosages should generally be reduced by 50%. Titration and maintenance dosages may be adjusted according to clinical response [see Use in Specific Populations (8.6) and Clinical Pharmacology (12.3)].

2.5 Patients with Hepatic Impairment

Dose adjustments are not required in patients with mild to moderate hepatic impairment. Use of APTIOM in patients with severe hepatic impairment has not been studied, and use in these patients is not recommended [see Use in Specific Populations (8.7) and Clinical Pharmacology (12.3)].

2.6 Discontinuation of APTIOM

When discontinuing APTIOM, reduce the dosage gradually and avoid abrupt discontinuation in order to minimize the risk of increased seizure frequency and status epilepticus [see Warnings and Precautions (5.7)].

3 DOSAGE FORMS AND STRENGTHS

APTIOM tablets are available in the following shapes and color (Table 2) with respective one-sided engraving:

Table 2: APTIOM Tablet Presentations
Tablet Strength | Tablet Color/Shape | Tablet Markings | Functional Score
200 mg | White oblong | ESL 200 | Yes
400 mg | White circular bi-convex | ESL 400 | No
600 mg | White oblong | ESL 600 | Yes
800 mg | White oblong | ESL 800 | Yes

4 CONTRAINDICATIONS

APTIOM is contraindicated in patients with a hypersensitivity to eslicarbazepine acetate or oxcarbazepine [see Warnings and Precautions (5.2, 5.3, and 5.4)].

5 WARNINGS AND PRECAUTIONS

5.1 Suicidal Behavior and Ideation

Antiepileptic drugs (AEDs), including APTIOM, increase the risk of suicidal thoughts or behavior in patients taking these drugs for any indication. Patients treated with any AED for any indication should be monitored for the emergence or worsening of depression, suicidal thoughts or behavior, and/or any unusual changes in mood or behavior.

Pooled analyses of 199 placebo-controlled clinical trials (mono- and adjunctive therapy) of 11 different AEDs showed that patients randomized to one of the AEDs had approximately twice the risk (adjusted Relative Risk 1.8, 95% confidence interval [CI]: 1.2, 2.7) of suicidal thinking or behavior compared to patients randomized to placebo. In these trials, which had a median treatment duration of 12 weeks, the estimated incidence of suicidal behavior or ideation among 27,863 AED-treated patients was 0.43%, compared to 0.24% among 16,029 placebo-treated patients, representing an increase of approximately one case of suicidal thinking or behavior for every 530 patients treated. There were four suicides in drug-treated patients in the trials and none in placebo-treated patients, but the number of events is too small to allow any conclusion about drug effect on suicide.

The increased risk of suicidal thoughts or behavior with AEDs was observed as early as one week after starting treatment with AEDs and persisted for the duration of treatment assessed. Because most trials included in the analysis did not extend beyond 24 weeks, the risk of suicidal thoughts or behavior beyond 24 weeks could not be assessed.

The risk of suicidal thoughts or behavior was generally consistent among drugs in the data analyzed. The finding of increased risk with AEDs of varying mechanisms of action and across a range of indications suggests that the risk applies to all AEDs used for any indication. The risk did not vary substantially by age (5-100 years) in the clinical trials analyzed.

Table 3 shows absolute and relative risk by indication for all evaluated AEDs.

Table 3: Risk of Suicidal Thoughts or Behaviors by Indication for Antiepileptic Drugs in the Pooled Analysis
Indication | Placebo Patients with Events Per 1000 Patients | Drug Patients with Events Per 1000 Patients | Relative Risk: Incidence of Events in Drug Patients/Incidence in Placebo Patients | Risk Differences: Additional Drug Patients with Events Per 1000 Patients
Epilepsy | 1.0 | 3.4 | 3.5 | 2.4
Psychiatric | 5.7 | 8.5 | 1.5 | 2.9
Other | 1.0 | 1.8 | 1.9 | 0.9
Total | 2.4 | 4.3 | 1.8 | 1.9

The relative risk for suicidal thoughts or behavior was higher in clinical trials in patients with epilepsy than in clinical trials in patients with psychiatric or other conditions, but the absolute risk differences were similar for epilepsy and psychiatric indications.

Anyone considering prescribing APTIOM or any other AED must balance this risk with the risk of untreated illness. Epilepsy and many other illnesses for which AEDs are prescribed are themselves associated with morbidity and mortality and an increased risk of suicidal thoughts and behavior. Should suicidal thoughts and behavior emerge during treatment, the prescriber needs to consider whether the emergence of these symptoms in any given patient may be related to the illness being treated.

Patients, their caregivers, and families should be informed that AEDs increase the risk of suicidal thoughts and behavior and should be advised of the need to be alert for the emergence or worsening of the signs and symptoms of depression; any unusual changes in mood or behavior; or the emergence of suicidal thoughts, behavior, or thoughts about self-harm. Behaviors of concern should be reported immediately to healthcare providers.

5.2 Serious Dermatologic Reactions

Serious dermatologic reactions including Stevens-Johnson Syndrome (SJS) and toxic epidermal necrolysis (TEN) have been reported in association with APTIOM use. Serious and sometimes fatal dermatologic reactions, including TEN and SJS, have also been reported in patients using oxcarbazepine or carbamazepine which are chemically related to APTIOM. The reporting rate of these reactions associated with oxcarbazepine use exceeds the background incidence rate estimates by a factor of 3- to 10-fold. The reporting rates for Aptiom have not been determined.

Risk factors for the development of serious and potentially fatal dermatologic reactions with APTIOM use have not been identified.

If a patient develops a dermatologic reaction while taking APTIOM, discontinue APTIOM use, unless the reaction is clearly not drug-related. Patients with a prior dermatologic reaction with oxcarbazepine, carbamazepine, or APTIOM should ordinarily not be treated with APTIOM [see Contraindications (4)].

5.3 Drug Reaction with Eosinophilia and Systemic Symptoms (DRESS)/Multiorgan Hypersensitivity

Drug Reaction with Eosinophilia and Systemic Symptoms (DRESS), also known as Multiorgan Hypersensitivity, has been reported in patients taking APTIOM. DRESS may be fatal or life-threatening. DRESS typically, although not exclusively, presents with fever, rash, and/or lymphadenopathy, in association with other organ system involvement, such as hepatitis, nephritis, hematological abnormalities, myocarditis, or myositis sometimes resembling an acute viral infection. Eosinophilia is often present. Because this disorder is variable in its expression, other organ systems not noted here may be involved. It is important to note that early manifestations of hypersensitivity, such as fever or lymphadenopathy, may be present even though rash is not evident. If such signs or symptoms are present, the patient should be evaluated immediately. APTIOM should be discontinued and not be resumed if an alternative etiology for the signs or symptoms cannot be established. Patients with a prior DRESS reaction with either oxcarbazepine or APTIOM should not be treated with APTIOM [see Contraindications (4)].

5.4 Anaphylactic Reactions and Angioedema

Rare cases of anaphylaxis and angioedema have been reported in patients taking APTIOM. Anaphylaxis and angioedema associated with laryngeal edema can be fatal. If a patient develops any of these reactions after treatment with APTIOM, the drug should be discontinued. Patients with a prior anaphylactic-type reaction with either oxcarbazepine or APTIOM should not be treated with APTIOM [see Contraindications (4)].

5.5 Hyponatremia

Clinically significant hyponatremia (sodium <125 mEq/L) can develop in patients taking APTIOM.

Measurement of serum sodium and chloride levels should be considered during maintenance treatment with APTIOM, particularly if the patient is receiving other medications known to decrease serum sodium levels, and should be performed if symptoms of hyponatremia develop (e.g., nausea/vomiting, malaise, headache, lethargy, confusion, irritability, muscle weakness/spasms, obtundation, or increase in seizure frequency or severity). Cases of symptomatic hyponatremia and syndrome of inappropriate antidiuretic hormone secretion (SIADH) have been reported during postmarketing use. In clinical trials, patients whose treatment with APTIOM was discontinued because of hyponatremia generally experienced normalization of serum sodium within a few days without additional treatment.

In the controlled adult adjunctive epilepsy trials, 4/415 patients (1.0%) treated with 800 mg and 6/410 (1.5%) patients treated with 1200 mg of APTIOM had at least one serum sodium value less than 125 mEq/L, compared to none of the patients assigned to placebo. A higher percentage of APTIOM-treated patients (5.1%) than placebo-treated patients (0.7%) experienced decreases in sodium values of more than 10 mEq/L. These effects were dose-related and generally appeared within the first 8 weeks of treatment (as early as after 3 days). Serious, life-threatening complications were reported with APTIOM-associated hyponatremia (as low as 112 mEq/L) including seizures, severe nausea/vomiting leading to dehydration, severe gait instability, and injury. Some patients required hospitalization and discontinuation of APTIOM. Concurrent hypochloremia was also present in patients with hyponatremia. Hyponatremia was also observed in adult monotherapy trials and in pediatric trials. Depending on the severity of hyponatremia, the dose of APTIOM may need to be reduced or discontinued.

5.6 Neurological Adverse Reactions

Dizziness and Disturbance in Gait and Coordination

APTIOM causes dose-related increases in adverse reactions related to dizziness and disturbance in gait and coordination (dizziness, ataxia, vertigo, balance disorder, gait disturbance, nystagmus, and abnormal coordination) [see Adverse Reactions (6.1)]. In controlled adult adjunctive epilepsy trials, these events were reported in 26% and 38% of patients randomized to receive APTIOM at doses of 800 mg and 1200 mg/day, respectively, compared to 12% of placebo-treated patients. Events related to dizziness and disturbance in gait and coordination were more often serious in APTIOM-treated patients than in placebo-treated patients (2% vs. 0%), and more often led to study withdrawal in APTIOM-treated patients than in placebo-treated patients (9% vs. 0.7%). There was an increased risk of these adverse reactions during the titration period (compared to the maintenance period) and there also may be an increased risk of these adverse reactions in patients 60 years of age and older compared to younger adults. Nausea and vomiting also occurred with these events. Adverse reactions related to dizziness and disturbance in gait and coordination were also observed in adult monotherapy trials and pediatric trials.

The incidence of dizziness was greater with the concomitant use of APTIOM and carbamazepine compared to the use of APTIOM without carbamazepine in adult and pediatric trials. Therefore, consider dosage modifications of both APTIOM and carbamazepine if these drugs are used concomitantly [see Dosage and Administration (2.3)].

Somnolence and Fatigue

APTIOM causes dose-dependent increases in somnolence and fatigue-related adverse reactions (fatigue, asthenia, malaise, hypersomnia, sedation, and lethargy). In the controlled adult adjunctive epilepsy trials, these events were reported in 13% of placebo patients, 16% of patients randomized to receive 800 mg/day APTIOM, and 28% of patients randomized to receive 1200 mg/day APTIOM. Somnolence and fatigue-related events were serious in 0.3% of APTIOM-treated patients (and 0 placebo patients) and led to discontinuation in 3% of APTIOM-treated patients (and 0.7% of placebo-treated patients). Somnolence and fatigue-related reactions were also observed in adult monotherapy trials and in pediatric trials.

Cognitive Dysfunction

APTIOM causes dose-dependent increases in cognitive dysfunction-related events in adults (memory impairment, disturbance in attention, amnesia, confusional state, aphasia, speech disorder, slowness of thought, disorientation, and psychomotor retardation). In the controlled adult adjunctive epilepsy trials, these events were reported in 1% of placebo patients, 4% of patients randomized to receive 800 mg/day APTIOM, and 7% of patients randomized to receive 1200 mg/day APTIOM. Cognitive dysfunction-related events were serious in 0.2% of APTIOM-treated patients (and 0.2% of placebo patients) and led to discontinuation in 1% of APTIOM-treated patients (and 0.5% of placebo-treated patients). Cognitive dysfunction events were also observed in adult monotherapy trials.

Visual Changes

APTIOM causes dose-dependent increases in events related to visual changes including diplopia, blurred vision, and impaired vision. In the controlled adult adjunctive epilepsy trials, these events were reported in 16% of patients randomized to receive APTIOM compared to 6% of placebo patients. Eye events were serious in 0.7% of APTIOM-treated patients (and 0 placebo patients) and led to discontinuation in 4% of APTIOM-treated patients (and 0.2% of placebo-treated patients). There was an increased risk of these adverse reactions during the titration period (compared to the maintenance period) and also in patients 60 years of age and older (compared to younger adults). The incidence of diplopia was greater with the concomitant use of APTIOM and carbamazepine compared to the use of APTIOM without carbamazepine (up to 16% vs. 6%, respectively) [see Dosage and Administration (2.3)]. Similar adverse reactions related to visual changes were also observed in adult monotherapy trials and in pediatric trials.

Hazardous Activities

Prescribers should advise patients against engaging in hazardous activities requiring mental alertness, such as operating motor vehicles or dangerous machinery, until the effect of APTIOM is known.

5.7 Withdrawal of AEDs

As with all antiepileptic drugs, APTIOM should be withdrawn gradually because of the risk of increased seizure frequency and status epilepticus, but if withdrawal is needed because of a serious adverse event, rapid discontinuation can be considered.

5.8 Drug Induced Liver Injury

Hepatic effects, ranging from mild to moderate elevations in transaminases (>3 times the upper limit of normal) to rare cases with concomitant elevations of total bilirubin (>2 times the upper limit of normal) have been reported with APTIOM use. Baseline evaluations of liver laboratory tests are recommended. The combination of transaminase elevations and elevated bilirubin without evidence of obstruction is generally recognized as an important predictor of severe liver injury. APTIOM should be discontinued in patients with jaundice or other evidence of significant liver injury (e.g., laboratory evidence).

5.9 Abnormal Thyroid Function Tests

Dose-dependent decreases in serum T3 and T4 (free and total) values have been observed in patients taking APTIOM. These changes were not associated with other abnormal thyroid function tests suggesting hypothyroidism. Abnormal thyroid function tests should be clinically evaluated.

5.10 Hematologic Adverse Reactions

Rare cases of pancytopenia, agranulocytosis, and leukopenia have been reported during postmarketing use in patients treated with APTIOM. Discontinuation of APTIOM should be considered in patients who develop pancytopenia, agranulocytosis, or leukopenia.

6 ADVERSE REACTIONS

The following adverse reactions are described in more detail in the Warnings and Precautions section of the label:

- Suicidal Behavior and Ideation [see Warnings and Precautions (5.1)]
- Serious Dermatologic Reactions [see Warnings and Precautions (5.2)]
- Drug Reaction with Eosinophilia and Systemic Symptoms (DRESS)/Multiorgan Hypersensitivity [see Warnings and Precautions (5.3)]
- Anaphylactic Reactions and Angioedema [see Warnings and Precautions (5.4)]
- Hyponatremia [see Warnings and Precautions (5.5)]
- Neurological Adverse Reactions [see Warnings and Precautions (5.6)]
- Drug Induced Liver Injury [see Warnings and Precautions (5.8)]
- Abnormal Thyroid Function Tests [see Warnings and Precautions (5.9)]
- Pancytopenia, Agranulocytosis, and Leukopenia [see Warnings and Precautions (5.10)]

6.1 Clinical Trials Experience

Because clinical trials are conducted under widely varying conditions, adverse reaction rates observed in the clinical trials of a drug cannot be directly compared to rates in the clinical trials of another drug and may not reflect the rates observed in practice.

Adult Patients

In monotherapy trials in patients with partial-onset seizures [Study 1 and Study 2, see Clinical Studies (14.1)], 365 patients received APTIOM, of whom 225 were treated for longer than 12 months and 134 for longer than 24 months. Of the patients in those trials, 95% were between 18 and 65 years old; 48% were male, and 84% were Caucasian. Across controlled and uncontrolled trials in patients receiving adjunctive therapy for partial-onset seizures, 1195 patients received APTIOM, of whom 586 were treated for longer than 6 months and 462 for longer than 12 months. In the placebo controlled adjunctive therapy trials in patients with partial-onset seizures (Study 3, Study 4 and Study 5), 1021 patients received APTIOM. Of the patients in those trials, approximately 95% were between 18 and 60 years old, approximately 50% were male, and approximately 80% were Caucasian.

Monotherapy Historical Control Trials

In the monotherapy epilepsy trials (Study 1 and Study 2), 13% of patients randomized to receive APTIOM at the recommended doses of 1200 mg and 1600 mg once daily discontinued from the trials as a result of an adverse event. The adverse reaction most commonly (≥1% on APTIOM) leading to discontinuation was hyponatremia.

Adverse reactions observed in these studies were generally similar to those observed and attributed to drug in adjunctive placebo-controlled studies. Because these studies did not include a placebo control group, causality could not be established.

Dizziness, nausea, somnolence, and fatigue were all reported at lower incidences during the AED Withdrawal Phase and Monotherapy Phase compared with the Titration Phase.

Adjunctive Therapy Controlled Trials

In the controlled adjunctive therapy epilepsy trials (Study 3, Study 4, and Study 5), the rate of discontinuation as a result of any adverse reaction was 14% for the 800 mg dose, 25% for the 1200 mg dose, and 7% in subjects randomized to placebo. The adverse reactions most commonly (≥1% in any APTIOM treatment group, and greater than placebo) leading to discontinuation, in descending order of frequency, were dizziness, nausea, vomiting, ataxia, diplopia, somnolence, headache, blurred vision, vertigo, asthenia, fatigue, rash, dysarthria, and tremor.

The most frequently reported adverse reactions in patients receiving APTIOM at doses of 800 mg or 1200 mg (≥4% and ≥2% greater than placebo) were dizziness, somnolence, nausea, headache, diplopia, vomiting, fatigue, vertigo, ataxia, blurred vision, and tremor.

Table 4 gives the incidence of adverse reactions that occurred in ≥2% of subjects with partial-onset seizures in any APTIOM treatment group and for which the incidence was greater than placebo during the controlled clinical trials. Adverse reactions during titration were less frequent for patients who began therapy at an initial dose of 400 mg for 1 week and then increased to 800 mg compared to patients who initiated therapy at 800 mg.

Table 4: Adverse Reactions Incidence in Pooled Controlled Clinical Trials of Adjunctive Therapy in Adults (Events ≥2% of Patients in the APTIOM 800 mg or 1200 mg Dose Group and More Frequent Than in the Placebo Group)
 | Placebo | APTIOM
 | Placebo | 800 mg | 1200 mg
 | (N=426) % | (N=415) % | (N=410) %
Ear and labyrinth disorders Vertigo | <1 | 2 | 6
Eye disorders Diplopia Blurred vision Visual impairment | 2 1 1 | 9 6 2 | 11 5 1
Gastrointestinal disorders Nausea Vomiting Diarrhea Constipation Abdominal pain Gastritis | 5 3 3 1 1 <1 | 10 6 4 2 2 2 | 16 10 2 2 2 <1
General disorders and administration site conditions Fatigue Asthenia Gait disturbance Peripheral edema | 4 2 <1 1 | 4 2 2 2 | 7 3 2 1
Infections and Infestations Urinary tract infections | 1 | 2 | 2
Injury, poisoning and procedural complications Fall | 1 | 3 | 1
Metabolism and nutrition disorders Hyponatremia | <1 | 2 | 2
Nervous system disorders Dizziness Somnolence Headache Ataxia Balance disorder Tremor Dysarthria Memory impairment Nystagmus | 9 8 9 2 <1 1 0 <1 <1 | 20 11 13 4 3 2 1 1 1 | 28 18 15 6 3 4 2 2 2
Psychiatric disorders Depression Insomnia | 2 1 | 1 2 | 3 2
Respiratory, thoracic and mediastinal disorders Cough | 1 | 2 | 1
Skin and subcutaneous tissue disorders Rash | 1 | 1 | 3
Vascular disorders Hypertension | 1 | 1 | 2

Pediatric Patients (4 to 17 Years of Age)

Clinical studies of pediatric patients 4 to 17 years of age were conducted which support the safety and tolerability of APTIOM for the treatment of partial-onset seizures. Across studies in pediatric patients with partial-onset seizures, 393 patients ages 4 to 17 years received APTIOM, of whom 265 received APTIOM for at least 1 year. Adverse reactions reported in clinical studies of pediatric patients 4 to 17 years of age were similar to those seen in adult patients.

Other Adverse Reactions with APTIOM Use

Compared to placebo, APTIOM use was associated with slightly higher frequencies of decreases in hemoglobin and hematocrit, increases in total cholesterol, triglycerides, and LDL, and increases in creatine phosphokinase.

Adverse Reactions Based on Gender and Race

No significant gender differences were noted in the incidence of adverse reactions. Although there were few non-Caucasian patients, no differences in the incidences of adverse reactions compared to Caucasian patients were observed.

6.2 Postmarketing Experience

The following adverse reactions have been identified during postapproval use of APTIOM. Because these reactions are reported voluntarily from a population of uncertain size, it is not always possible to reliably estimate their frequency or establish a causal relationship to drug exposure:

Hematologic and Lymphatic Systems: leukopenia, agranulocytosis, thrombocytopenia, megaloblastic anemia, and pancytopenia [see Warnings and Precautions (5.10)]

Metabolism and Nutrition Disorders: syndrome of inappropriate antidiuretic hormone secretion (SIADH) [see Warnings and Precautions (5.5)]

7 DRUG INTERACTIONS

7.1 Other Antiepileptic Drugs

Several AEDs (e.g., carbamazepine, phenobarbital, phenytoin, and primidone) can induce enzymes that metabolize APTIOM and can cause decreased plasma concentrations of eslicarbazepine [see Clinical Pharmacology (12.3)]. Higher doses of Aptiom may be needed [see Dosage and Administration (2.4)].

7.2 CYP2C19 Substrates

APTIOM can inhibit CYP2C19, which can cause increased plasma concentrations of drugs that are metabolized by this isoenzyme (e.g., phenytoin, clobazam, and omeprazole) [see Clinical Pharmacology (12.3)]. Dose adjustment may be needed.

7.3 CYP3A4 Substrates

In vivo studies suggest that APTIOM can induce CYP3A4, decreasing plasma concentrations of drugs that are metabolized by this isoenzyme (e.g., simvastatin, lovastatin) [see Clinical Pharmacology (12.3)]. Dose adjustment of simvastatin and lovastatin may be needed if a clinically significant change in lipids is noted.

7.4 Oral Contraceptives

Because concomitant use of APTIOM and ethinylestradiol and levonorgestrel is associated with lower plasma levels of these hormones, females of reproductive potential should use additional or alternative non-hormonal birth control.

8 USE IN SPECIFIC POPULATIONS

8.1 Pregnancy

Pregnancy Exposure Registry

There is a pregnancy exposure registry that monitors pregnancy outcomes in women exposed to AEDs, such as APTIOM, during pregnancy. Encourage women who are taking APTIOM during pregnancy to enroll in the North American Antiepileptic Drug (NAAED) Pregnancy Registry by calling 1-888-233-2334 or visiting http://www.aedpregnancyregistry.org.

Risk Summary

Limited available data with APTIOM use in pregnant women are insufficient to inform a drug-associated risk of adverse developmental outcomes. In oral studies conducted in pregnant mice, rats, and rabbits, eslicarbazepine acetate demonstrated developmental toxicity, including increased incidence of malformations (mice), embryolethality (rats), and fetal growth retardation (all species), at clinically relevant doses (see Data). Advise a pregnant woman of the potential risk to a fetus.

In the U.S. general population, the estimated background risk of major birth defects and miscarriage in clinically recognized pregnancies is 2-4% and 15-20%, respectively. The background risk of major birth defects and miscarriage for the indicated population is unknown.

Data

Animal Data

When eslicarbazepine acetate was orally administered (150, 350, 650 mg/kg/day) to pregnant mice throughout organogenesis, increased incidences of fetal malformations was observed at all doses and fetal growth retardation was observed at the mid and high doses. A no-effect dose for adverse developmental effects was not identified. At the lowest dose tested, plasma eslicarbazepine exposure (Cmax, AUC) is less than that in humans at the maximum recommended human dose (MRHD, 1600 mg/day).

Oral administration of eslicarbazepine acetate (40, 160, 320 mg/kg/day) to pregnant rabbits throughout organogenesis resulted in fetal growth retardation and increased incidences of skeletal variations at the mid and high doses. The no-effect dose (40 mg/kg/day) is less than the MRHD on a mg/m^2 basis.

Oral administration to pregnant rats (65, 125, 250 mg/kg/day) throughout organogenesis resulted in embryolethality at all doses, increased incidences of skeletal variations at the mid and high doses, and fetal growth retardation at the high dose. The lowest dose tested (65 mg/kg/day) is less than the MRHD on a mg/m^2 basis.

When eslicarbazepine acetate was orally administered to female mice during pregnancy and lactation (150, 350, 650 mg/kg/day), the gestation period was prolonged at the highest dose tested. In offspring, a persistent reduction in offspring body weight and delayed physical development and sexual maturation were observed at the mid and high doses. The lowest dose tested (150 mg/kg/day) is less than the MRHD on a mg/m^2 basis.

When eslicarbazepine acetate was orally administered (65, 125, 250 mg/kg/day) to rats during pregnancy and lactation, reduced offspring body weight was seen at the mid and high doses. Delayed sexual maturation and a neurological deficit (decreased motor coordination) were observed at the highest dose tested. The no-effect dose for adverse developmental effects (65 mg/kg/day) is less than the MRHD on a mg/m^2 basis.

The rat data are of uncertain relevance to humans because of differences in metabolic profile between species.

8.2 Lactation

Eslicarbazepine is present in human milk. The effects of APTIOM on the breastfed infant or on milk production are unknown. The developmental and health benefits of breastfeeding should be considered along with the mother's clinical need for APTIOM and any potential adverse effects on the breastfed infant from APTIOM or from the underlying maternal condition.

8.3 Females and Males of Reproductive Potential

Contraception

Use of APTIOM with hormonal contraceptives containing ethinylestradiol or levonorgestrel is associated with lower plasma levels of these hormones. Advise women of reproductive potential taking APTIOM who are using a contraceptive containing ethinylestradiol or levonorgestrel to use additional or alternative non-hormonal birth control [see Drug Interactions (7.4)].

Infertility

Eslicarbazepine acetate was evaluated in rats and mice for potential adverse impact on fertility of the parental and first generation [see Nonclinical Toxicology (13.1)]. In a fertility study in male and female mice, adverse developmental outcomes were observed in embryos. In a fertility study in male and female rats, impairment of female fertility by eslicarbazepine acetate was shown.

8.4 Pediatric Use

Safety and effectiveness of APTIOM have been established in the age groups 4 to 17 years. Use of APTIOM in these age groups is supported by evidence from adequate and well-controlled studies of APTIOM in adults with partial-onset seizures, pharmacokinetic data from adult and pediatric patients, and safety data from clinical studies in 393 pediatric patients 4 to 17 years of age [see Adverse Reactions (6.1) and Clinical Pharmacology (12.3)].

Safety and effectiveness in pediatric patients below the age of 4 years have not been established.

Animal Data

In a juvenile animal study in which eslicarbazepine acetate (40, 80, 160 mg/kg/day) was orally administered to young dogs for 10 months starting on postnatal day 21, adverse effects on bone growth (decreased bone mineral content and density) were seen in females at all doses at the end of the dosing period, but not at the end of a 2-month recovery period. Convulsions were seen at the highest dose tested. A no-effect dose for adverse effects in juvenile dogs was not identified. The lowest dose tested is less than the maximum recommended pediatric dose (1200 mg/day) on a body surface area (mg/m^2) basis.

A separate juvenile animal study was conducted to assess possible adverse effects on the immune system. Eslicarbazepine acetate (10, 40, 80 mg/kg/day) was orally administered to young dogs for 17 weeks starting on postnatal day 21. No effects on the immune system were observed.

8.5 Geriatric Use

There were insufficient numbers of patients ≥65 years old enrolled in the controlled adjunctive epilepsy trials (N=15) to determine the efficacy of APTIOM in this patient population. The pharmacokinetics of APTIOM were evaluated in elderly healthy subjects (N=12) (Figure 1). Although the pharmacokinetics of eslicarbazepine are not affected by age independently, dose selection should take in consideration the greater frequency of renal impairment and other concomitant medical conditions and drug therapies in the elderly patient. Dose adjustment is necessary if CrCl is <50 mL/min [see Clinical Pharmacology (12.3)].

8.6 Patients with Renal Impairment

Clearance of eslicarbazepine is decreased in patients with impaired renal function and is correlated with creatinine clearance. Dosage adjustment is necessary in patients with CrCl<50 mL/min (Figure 1) [see Dosage and Administration (2.4) and Clinical Pharmacology (12.3)].

8.7 Patients with Hepatic Impairment

Dose adjustments are not required in patients with mild to moderate hepatic impairment (Figure 1). Use of APTIOM in patients with severe hepatic impairment has not been evaluated, and use in these patients is not recommended [see Clinical Pharmacology (12.3)].

9 DRUG ABUSE AND DEPENDENCE

9.1 Controlled Substance

APTIOM is not a controlled substance.

9.2 Abuse

Prescription drug abuse is the intentional non-therapeutic use of a drug, even once, for its rewarding psychological or physiological effects. Drug addiction, which develops after repeated drug abuse, is characterized by a strong desire to take a drug despite harmful consequences, difficulty in controlling its use, giving a higher priority to drug use than to obligations, increased tolerance, and sometimes physical withdrawal. Drug abuse and drug addiction are separate and distinct from physical dependence (for example, abuse may not be accompanied by physical dependence) [see Drug Abuse and Dependence (9.3)].

In a human abuse study in recreational sedative abusers APTIOM showed no evidence of abuse. In Phase 1, 1.5% of the healthy volunteers taking APTIOM reported euphoria compared to 0.4% taking placebo.

9.3 Dependence

Physical dependence is characterized by withdrawal symptoms after abrupt discontinuation or a significant dose reduction of a drug.

There was some evidence of physical dependence or a withdrawal syndrome with APTIOM in a physical dependence study conducted in healthy volunteers who were maintained at a daily dose of 800 mg APTIOM for 4 weeks prior to discontinuation. The primary endpoint was the maximum change from steady-state baseline in the total score of the Physician's Withdrawal Checklist (PWC-34) during the 21-day discontinuation period. APTIOM and placebo were shown to be equivalent on the primary endpoint. Two out of 8 secondary endpoints (visual analog scales for anxiety and nausea) showed some increase in these symptoms for subjects who were maintained on APTIOM and discontinued, versus subjects who were maintained on placebo. In general, AEDs should not be abruptly discontinued in patients with epilepsy because of the risk of increased seizure frequency and status epilepticus.

10 OVERDOSAGE

10.1 Signs, Symptoms, and Laboratory Findings of Acute Overdose in Humans

Symptoms of overdose are consistent with the known adverse reactions of APTIOM and include hyponatremia (sometimes severe), dizziness, nausea, vomiting, somnolence, euphoria, oral paraesthesia, ataxia, walking difficulties, and diplopia. The maximum dosage studied in open-label adult monotherapy treatment following withdrawal of concomitant AEDs was 2400 mg once daily.

10.2 Treatment or Management of Overdose

There is no specific antidote for overdose with APTIOM. Symptomatic and supportive treatment should be administered as appropriate. Removal of the drug by gastric lavage and/or inactivation by administering activated charcoal should be considered.

Standard hemodialysis procedures result in partial clearance of APTIOM. Hemodialysis may be considered based on the patient's clinical state or in patients with significant renal impairment.

11 DESCRIPTION

The chemical name of APTIOM (eslicarbazepine acetate) is (S)-10-Acetoxy-10,11-dihydro-5H-dibenz[b,f]azepine-5-carboxamide. APTIOM is a dibenz[b,f]azepine-5-carboxamide derivative. Its molecular formula is C17H16N2O3 and its molecular weight is 296.32. The chemical structure is:

APTIOM is a white to off-white, odorless crystalline solid. It is insoluble in hexane, very slightly soluble in aqueous solvents and soluble in organic solvents such as acetone, acetonitrile, and methanol.

Each APTIOM tablet contains 200 mg, 400 mg, 600 mg or 800 mg of eslicarbazepine acetate and the following inactive ingredients: croscarmellose sodium, magnesium stearate, and povidone.

12 CLINICAL PHARMACOLOGY

12.1 Mechanism of Action

APTIOM is extensively converted to eslicarbazepine, which is considered to be responsible for therapeutic effects in humans. The precise mechanism(s) by which eslicarbazepine exerts anticonvulsant activity is unknown but is thought to involve inhibition of voltage-gated sodium channels.

12.2 Pharmacodynamics

The effect of APTIOM on cardiac repolarization was evaluated in a randomized, double-blind, placebo- and active-controlled 4-period crossover trial in healthy adult men and women. Subjects received APTIOM 1200 mg once daily × 5 days, APTIOM 2400 mg once daily × 5 days, an active-control, moxifloxacin 400 mg × 1 dose on Day 5, and placebo once daily × 5 days. At both doses of APTIOM, no significant effect on the QTc interval was detected.

12.3 Pharmacokinetics

The pharmacokinetics of eslicarbazepine is linear and dose-proportional in the dose range of 400 mg to 1600 mg once daily, both in healthy adult subjects and patients. The apparent half-life of eslicarbazepine in plasma was 13-20 hours in adult epilepsy patients. Steady-state plasma concentrations are attained after 4 to 5 days of once daily dosing.

Absorption, Distribution, Metabolism, and Excretion

Absorption

APTIOM is mostly undetectable (0.01% of the systemic exposure) after oral administration. Eslicarbazepine, the major metabolite, is primarily responsible for the pharmacological effect of APTIOM. Peak plasma concentrations (Cmax) of eslicarbazepine are attained at 1-4 hours post-dose. Eslicarbazepine is highly bioavailable, because the amount of eslicarbazepine and glucuronide metabolites recovered in urine corresponded to more than 90% of an APTIOM dose. Food has no effect on the pharmacokinetics of eslicarbazepine after oral administration of APTIOM.

Distribution

The binding of eslicarbazepine to plasma proteins is relatively low (<40%) and independent of concentration. In vitro studies have shown that plasma protein binding was not relevantly affected by the presence of warfarin, diazepam, digoxin, phenytoin, or tolbutamide. Similarly, the binding of warfarin, diazepam, digoxin, phenytoin or tolbutamide was not significantly affected by the presence of eslicarbazepine. The apparent volume of distribution of eslicarbazepine is 61 L for body weight of 70 kg based on population PK analysis.

Metabolism

APTIOM is rapidly and extensively metabolized to its major active metabolite eslicarbazepine by hydrolytic first-pass metabolism. Eslicarbazepine corresponds to 91% of systemic exposure. The systemic exposure to minor active metabolites of (R)-licarbazepine is 5% and oxcarbazepine is 1%. The inactive glucuronides of these active metabolites correspond to approximately 3% of systemic exposure.

In in vitro studies in human liver microsomes, eslicarbazepine had no clinically relevant inhibitory effect on the activity of CYP1A2, CYP2A6, CYP2B6, CYP2D6, CYP2E1, and CYP3A4, and only a moderate inhibitory effect on CYP2C19. Studies with eslicarbazepine in fresh human hepatocytes showed no induction of enzymes involved in glucuronidation and sulfation of 7-hydroxy-coumarin. A mild activation of UGT1A1-mediated glucuronidation was observed in human hepatic microsomes.

No apparent autoinduction of metabolism has been observed with APTIOM in humans.

Excretion

APTIOM metabolites are eliminated from the systemic circulation primarily by renal excretion, in the unchanged and glucuronide conjugate forms. In total, eslicarbazepine and its glucuronide account for more than 90% of total metabolites excreted in urine, approximately two thirds in the unchanged form and one third as glucuronide conjugate. Other minor metabolites account for the remaining 10% excreted in the urine. In healthy subjects with normal renal function, the renal clearance of eslicarbazepine (approximately 20 mL/min) is substantially lower than glomerular filtration rate (80-120 mL/min), suggesting that renal tubular reabsorption occurs. The apparent plasma half-life of eslicarbazepine was 13-20 hours in epilepsy patients [see Dosage and Administration (2.4) and Use in Specific Populations (8.6)].

Specific Populations

Geriatric Patients (≥65 Years of Age)

The pharmacokinetic profile of eslicarbazepine was unaffected in elderly subjects with creatinine clearance >60 mL/min compared to healthy subjects (18-40 years) after single and repeated doses of 600 mg APTIOM during 8 days of dosing. No dose adjustment is necessary in adults based on age, if CrCl is ≥50 mL/min.

Pediatric Patients (4 to 17 Years of Age)

A pharmacokinetic study of APTIOM was performed in 29 pediatric patients with partial-onset seizures. Limited pharmacokinetic sampling was also performed during controlled pediatric adjunctive therapy partial-onset seizure studies. As in adult patients, APTIOM is rapidly and extensively metabolized to its major active metabolite eslicarbazepine. The pharmacokinetics of eslicarbazepine is linear and dose-proportional in the dose range of 5 to 30 mg/kg/day. Peak plasma concentrations (Cmax) of eslicarbazepine are attained at 1-3 hours post-dose.

A population pharmacokinetic analysis showed that body weight significantly correlates with the clearance of eslicarbazepine in pediatric patients; clearance increased with an increase in body weight. A weight-based dosing regimen is necessary to achieve eslicarbazepine exposures in pediatric patients aged 4 to 17 years similar to those observed in adults treated at effectives doses of APTIOM [see Dosage and Administration (2.2)]. The apparent half-life of eslicarbazepine in plasma was 10-16 hours in pediatric patients with partial-onset seizures. Steady-state plasma concentrations are attained after 4 to 5 days of once- daily dosing.

The pharmacokinetics of eslicarbazepine in pediatric patients are similar when used as monotherapy or as adjunctive therapy for the treatment of partial-onset seizures.

Gender

Studies in healthy subjects and patients showed that pharmacokinetics of eslicarbazepine was not affected by gender.

Race

No clinically significant effect of race (Caucasian N=849, Black N=53, Asian N=65, and Other N=51) on the pharmacokinetics of eslicarbazepine was noted in a population pharmacokinetic analysis of pooled data from the clinical studies.

Renal Impairment

APTIOM metabolites are eliminated from the systemic circulation primarily by renal excretion. The extent of systemic exposure of eslicarbazepine following an 800 mg single dose was increased by 62% in patients with mild renal impairment (CrCl 50-80 mL/min), by 2-fold in patients with moderate renal impairment (CrCl 30-49 mL/min) and by 2.5-fold in patients with severe renal impairment (CrCl <30 mL/min) in comparison to the healthy subjects (CrCl >80 mL/min). Dosage adjustment is recommended in patients with creatinine clearance below 50 mL/min [see Dosage and Administration (2.4) and Use in Specific Populations (8.6)].

In patients with end stage renal disease, repeated hemodialysis removed APTIOM metabolites from systemic circulation.

Hepatic Impairment

The pharmacokinetics and metabolism of APTIOM was evaluated in healthy subjects and patients with moderate liver impairment (7-9 points on the Child-Pugh assessment) after multiple oral doses (see Figure 1). Moderate hepatic impairment did not affect the pharmacokinetics of APTIOM. No dose adjustment is recommended in patients with mild to moderate liver impairment.

The pharmacokinetics of APTIOM has not been studied in patients with severe hepatic impairment.

Figure 1: Impact of Intrinsic Factors on AUC of Eslicarbazepine

Drug Interaction Studies

Potential for Other AEDs to Affect Eslicarbazepine

The potential impact of other AEDs on the systemic exposure (area under the curve, AUC) of eslicarbazepine, the active metabolite of APTIOM, is shown in Figure 2:

Figure 2: Potential Impact of Other AEDs on AUC of Eslicarbazepine

Potential for APTIOM to Affect Other Drugs

The potential impact of APTIOM on the systemic exposure (AUC) of other drugs (including AEDs) is shown in Figures 3a and 3b:

Figure 3a: Potential Impact of APTIOM on the AUC of AEDs

Figure 3b: Potential Impact of APTIOM on the AUC of Non-AEDs

13 NONCLINICAL TOXICOLOGY

13.1 Carcinogenesis, Mutagenesis, Impairment of Fertility

Carcinogenesis

In a two-year carcinogenicity study in mice, eslicarbazepine acetate was administered orally at doses of 100, 250, and 600 mg/kg/day. An increase in the incidence of hepatocellular adenomas and carcinomas was observed at 250 and 600 mg/kg/day in males and at 600 mg/kg/day in females. The dose not associated with an increase in tumors (100 mg/kg/day) is less than the MRHD (1600 mg/day for monotherapy) on a mg/m^2 basis.

Mutagenesis

Eslicarbazepine acetate and eslicarbazepine were not mutagenic in the in vitro Ames assay. In in vitro assays in mammalian cells, eslicarbazepine acetate and eslicarbazepine were not clastogenic in human peripheral blood lymphocytes; however, eslicarbazepine acetate was clastogenic in Chinese hamster ovary (CHO) cells, with and without metabolic activation. Eslicarbazepine acetate was positive in the in vitro mouse lymphoma tk assay in the absence of metabolic activation. Eslicarbazepine acetate was not clastogenic in the in vivo mouse micronucleus assay.

Impairment of Fertility

When eslicarbazepine acetate (150, 350, and 650 mg/kg/day) was orally administered to male and female mice prior to and throughout the mating period, and continuing in females to gestation day 6, there was an increase in embryolethality at all doses. The lowest dose tested is less than the MRHD on a mg/m^2 basis.

When eslicarbazepine acetate (65, 125, 250 mg/kg/day) was orally administered to male and female rats prior to and throughout the mating period, and continuing in females to implantation, lengthening of the estrus cycle was observed at the highest dose tested. The data in rats are of uncertain relevance to humans because of differences in metabolic profile between species.

14 CLINICAL STUDIES

14.1 Monotherapy for Partial-Onset Seizures

The effectiveness of APTIOM as monotherapy for partial-onset seizures was established in two identical, dose-blinded historical control trials in a total of 365 patients with epilepsy (Study 1 and Study 2). In these trials, patients were randomized in a 2:1 ratio to receive either APTIOM 1600 mg or 1200 mg once daily, and their responses were compared to those of a historical control group. The historical control methodology is described in a publication by French et al. [see References (15)]. The historical control consisted of a pooled analysis of the control groups from 8 trials of similar design, which utilized a subtherapeutic dose of an AED as a comparator. Statistical superiority to the historical control was considered to be demonstrated if the upper limit from a 2-sided 95% confidence interval for the percentage of patients meeting exit criteria in patients receiving APTIOM remained below the lower 95% prediction interval of 65% derived from the historical control data.

In Study 1 and Study 2, patients ≥16 years of age experienced at least 4 seizures during the baseline period with no 28-day seizure free period while receiving 1 or 2 AEDs (both could not be sodium-channel blocking drugs, and at least one AED was limited to 2/3 of a typical dose). APTIOM was titrated over a 1- to 2-week period followed by the gradual withdrawal of the background AED over a 6-week period, followed by a 10-week monotherapy period.

The exit criteria were one or more of the following: (1) an episode of status epilepticus, (2) emergence of a generalized tonic-clonic seizure in patients who had not had one in the past 6 months, (3) doubling of average monthly seizure count during any 28 consecutive days, (4) doubling of highest consecutive 2-day seizure frequency during the entire treatment phase, or (5) worsening of seizure severity considered by the investigator to require intervention. The primary endpoint was the cumulative 112-day exit rate in the efficacy population. Additionally, in Studies 1 and 2, if the discontinuation rate exceeded 10%, patients were randomly reassigned to be counted as exits.

The most commonly used baseline AEDs were carbamazepine, levetiracetam, valproic acid, and lamotrigine. Oxcarbazepine was used as a baseline AED in 6.6% of patients.

In Study 1, the Kaplan-Meier (K-M) estimate of the percentage of patients meeting at least 1 exit criterion was 29% (95% CI: 21%, 38%) in the 1600 mg group and 44% (95% CI 33%, 58%) in the 1200 mg group. In Study 2, the K-M estimate of the percentage of patients meeting at least 1 exit criterion was 13% (95% CI: 8%, 22%) in the 1600 mg group and 16% (95% CI: 8%, 29%) in the 1200 mg group. The upper limit of the 2-sided 95% CI of both doses in both trials were below the threshold of 65% derived from the historical control data, meeting the pre-specified criteria for efficacy (see Figure 4).

Figure 4: Kaplan-Meier Estimates of Cumulative 112-Day Exit Rates for Studies 1 and 2

14.2 Adjunctive Therapy for Partial-Onset Seizures

The efficacy of APTIOM as adjunctive therapy in partial-onset seizures was established in three randomized, double-blind, placebo-controlled, multicenter trials in adult patients with epilepsy (Study 3, Study 4, and Study 5). Patients enrolled had partial-onset seizures with or without secondary generalization and were not adequately controlled with 1 to 3 concomitant AEDs. During an 8-week baseline period, patients were required to have an average of ≥4 partial-onset seizures per 28 days with no seizure-free period exceeding 21 days. In these three trials, patients had a median duration of epilepsy of 19 years and a median baseline seizure frequency of 8 seizures per 28 days. Two-thirds (69%) of subjects used 2 concomitant AEDs and 28% used 1 concomitant AED. The most commonly used AEDs were carbamazepine (50%), lamotrigine (24%), valproic acid (21%), and levetiracetam (18%). Oxcarbazepine was not allowed as a concomitant AED.

Studies 3 and 4 compared dosages of APTIOM 400, 800, and 1200 mg once daily with placebo. Study 5 compared dosages of APTIOM 800 and 1200 mg once daily with placebo. In all three trials, following an 8-week Baseline Phase, which established a baseline seizure frequency, subjects were randomized to a treatment arm. Patients entered a treatment period consisting of an initial titration phase (2 weeks), and a subsequent maintenance phase (12 weeks). The specific titration schedule differed amongst the three studies. Thus, patients were started on a daily dose of 400 mg or 800 mg and subsequently increased by 400 mg/day following one or two weeks, until the final daily target dose was achieved.

The standardized seizure frequency during the Maintenance Phase over 28 days was the primary efficacy endpoint in all three trials. Table 5 presents the results for the primary endpoint, as well as the secondary endpoint of percent reduction from baseline in seizure frequency. The APTIOM treatment at 400 mg/day was studied in Studies 3 and 4 and did not show significant treatment effect. A statistically significant effect was observed with APTIOM treatment at doses of 800 mg/day in Studies 3 and 4, but not in Study 5, and at doses of 1200 mg/day in all 3 studies.

Table 5: Standardized Seizure Frequency During the Maintenance Phase Over 28 Days and Percent Reduction from Baseline in Seizure Frequency
 | Placebo | APTIOM
 | Placebo | 800 mg | 1200 mg
Study 3
N | 95 | 88 | 87
Seizure Frequency (LS Mean seizures per 28 days) (p-value) | 6.6 | 5.0 (0.047*) | 4.3 (0.001*)
Median Percent Reduction from Baseline in Seizure Frequency (%) | -15 | -36 | -39
Study 4
N | 99 | 87 | 81
Seizure Frequency (LS Mean seizures per 28 days) (p-value) | 8.6 | 6.2 (0.006*) | 6.6 (0.042*)
Median Percent Reduction from Baseline in Seizure Frequency (%) | -6 | -33 | -28
Study 5
N | 212 | 200 | 184
Seizure Frequency (LS Mean seizures per 28 days) (p-value) | 7.9 | 6.5 (0.058) | 6.0 (0.004*)
Median Percent Reduction from Baseline in Seizure Frequency (%) | -22 | -30 | -36
*statistically significant compared to placebo

Figure 5 shows changes from baseline in the 28-day total partial seizure frequency by category of reduction in seizure frequency from baseline for patients treated with APTIOM and placebo in an integrated analysis across the three clinical trials. Patients in whom the seizure frequency increased are shown to the left as “Worse.” Patients in whom the seizure frequency decreased are shown in four categories.

Figure 5: Proportion of Patients by Category of Seizure Reduction for APTIOM and Placebo Across All Three Double-blind Trials

15 REFERENCES

French JA, Wang S, Warnock B, Temkin N. Historical control monotherapy design in the treatment of epilepsy. Epilepsia 2010;51(10):1936-43.

16 HOW SUPPLIED/STORAGE AND HANDLING

16.1 How Supplied

APTIOM tablets are white, oblong and with functional scoring on one side (200 mg, 600 mg, and 800 mg) or white, circular bi-convex and plain on one side (400 mg) and identified with strength-specific one-sided engraving on the other side, “ESL 200” (200 mg), “ESL 400” (400 mg), “ESL 600” (600 mg), or “ESL 800” (800 mg). Tablets are supplied in the following strengths and package configurations (Table 6):

Table 6: Package Configuration for APTIOM Tablets
Tablet Strength | Package Configuration | NDC Code
200 mg | Bottles of 30 | 63402-202-30
400 mg | Bottles of 30 | 63402-204-30
600 mg | Bottles of 60 | 63402-206-60
800 mg | Bottles of 30 | 63402-208-30

16.2 Storage and Handling

Store APTIOM tablets at 20°C to 25°C (68°F to 77°F); excursions permitted to 15°C to 30°C (59°F to 86°F) [see USP Controlled Room Temperature].

17 PATIENT COUNSELING INFORMATION

See FDA-approved patient labeling (Medication Guide).

Inform patients and caregivers of the availability of a Medication Guide, and instruct them to read the Medication Guide prior to taking APTIOM. Instruct patients and caregivers that APTIOM should only be taken as prescribed.

Suicidal Behavior and Ideation

Counsel patients, their caregivers, and families that AEDs, including APTIOM, may increase the risk of suicidal thoughts and behavior and advise them of the need to be alert for the emergence or worsening of symptoms of depression, any unusual changes in mood or behavior, or the emergence of suicidal thoughts, behavior, or thoughts about self-harm. Instruct patients, caregivers, and families to report behaviors of concern immediately to healthcare providers [see Warnings and Precautions (5.1)].

Serious Dermatologic Reactions

Advise patients and caregivers about the risk of potentially fatal serious skin reactions. Educate patients and caregivers about the signs and symptoms that may signal a serious skin reaction. Instruct patients and caregivers to consult with their healthcare provider immediately if a skin reaction occurs during treatment with APTIOM [see Warnings and Precautions (5.2)].

DRESS/Multi-organ Hypersensitivity

Instruct patients and caregivers that a fever associated with signs of other organ system involvement (e.g., rash, lymphadenopathy, hepatic dysfunction) may be drug-related and should be reported to their healthcare provider immediately [see Warnings and Precautions (5.3)].

Anaphylactic Reactions and Angioedema

Advise patients and caregivers of life threatening symptoms suggesting anaphylaxis or angioedema (swelling of the face, eyes, lips, tongue, or difficulty in swallowing or breathing) that can occur with APTIOM. Instruct them to immediately report these symptoms to their healthcare provider [see Warnings and Precautions (5.4)].

Hyponatremia

Advise patients and caregivers that APTIOM may reduce serum sodium concentrations, especially if they are taking other medications that can lower sodium. Advise patients and caregivers to report symptoms of low sodium such as nausea, tiredness, lack of energy, irritability, confusion, muscle weakness/spasms, or more frequent or more severe seizures [see Warnings and Precautions (5.5)].

Neurological Adverse Reactions

Counsel patients and caregivers that APTIOM may cause dizziness, gait disturbance, somnolence/fatigue, cognitive dysfunction, and visual changes. These adverse reactions, if observed, are more likely to occur during the titration period compared to the maintenance period. Advise patients not to drive or operate machinery until they have gained sufficient experience on APTIOM to gauge whether it adversely affects their ability to drive or operate machinery [see Warnings and Precautions (5.6)].

Withdrawal of APTIOM

Advise patients and caregivers not to discontinue use of APTIOM without consulting with their healthcare provider. APTIOM should be gradually withdrawn to minimize the potential of increased seizure frequency and status epilepticus [see Warnings and Precautions (5.7)].

Hematologic Adverse Reactions

Advise patients and caregivers that there have been rare reports of blood disorders reported in patients treated with APTIOM. Instruct patients to immediately consult with their physician if they experience symptoms suggestive of blood disorders [see Warnings and Precautions (5.10)].

Interaction with Oral Contraceptives

Inform patients and caregivers that APTIOM can significantly decrease the effectiveness of hormonal contraceptives. Recommend that female patients of childbearing potential use additional or alternative non-hormonal forms of contraception during treatment with APTIOM and after treatment has been discontinued for at least one menstrual cycle or until otherwise instructed by their healthcare provider [see Drug Interactions (7.3, 7.4)].

Pregnancy Registry

Encourage patients to enroll in the North American Antiepileptic Drug Pregnancy Registry if they become pregnant. This Registry is collecting information about the safety of AEDs during pregnancy. To enroll, patients can call 1-888-233-2334 (toll-free) [see Use in Specific Populations (8.1)].

Manufactured for:
Sumitomo Pharma America, Inc.
Marlborough, MA 01752 USA

Under license from

© 2023 Sumitomo Pharma America, Inc. All rights reserved.

10018-03

MEDICATION GUIDE
APTIOM (ap tee' om)
(eslicarbazepine acetate)
tablets

What is the most important information I should know about APTIOM?

- Do not stop taking APTIOM without first talking to your healthcare provider.
  - Stopping APTIOM suddenly can cause serious problems. Stopping a seizure medicine suddenly in a patient who has epilepsy may cause seizures that will not stop (status epilepticus).

1. Like other antiepileptic drugs, APTIOM may cause suicidal thoughts or actions in a very small number of people, about 1 in 500.
Call a healthcare provider right away if you have any of these symptoms, especially if they are new, worse, or worry you:

- thoughts about suicide or dying
- new or worse depression
- feeling agitated or restless
- trouble sleeping (insomnia)
- acting aggressive, being angry, or violent
- an extreme increase in activity and talking (mania)

- attempt to commit suicide
- new or worse anxiety
- panic attacks
- new or worse irritability
- acting on dangerous impulses
- other unusual changes in behavior or mood

How can I watch for early symptoms of suicidal thoughts and actions?

- Pay attention to any changes, especially sudden changes, in mood, behaviors, thoughts, or feelings.
- Keep all follow-up visits with your healthcare provider as scheduled.
- Call your healthcare provider between visits as needed, especially if you are worried about symptoms.
  Suicidal thoughts or actions may be caused by things other than medicines. If you have suicidal thoughts or actions, your healthcare provider may check for other causes.

2. APTIOM may cause allergic reactions or serious problems which may affect organs and other parts of your body like the liver or blood cells. You may or may not have a rash with these types of reactions.
Call your healthcare provider right away if you have any of the following:

- swelling of your face, eyes, lips, or tongue
- a skin rash
- fever, swollen glands, or sore throat that do not go away or come and go
- yellowing of your skin or eyes
- severe fatigue or weakness
- frequent infections or infections that do not go away

- trouble swallowing or breathing
- hives
- painful sores in the mouth or around your eyes
- unusual bruising or bleeding
- severe muscle pain

- APTIOM may cause the level of sodium in your blood to be low. Symptoms of low blood sodium include:

- nausea
- irritability
- muscle weakness or muscle spasms

- tiredness, lack of energy
- confusion
- more frequent or more severe seizures

Some medicines can also cause low sodium in your blood. Be sure to tell your healthcare provider about all the other medicines that you are taking.

What is APTIOM?
APTIOM is a prescription medicine used to treat partial-onset seizures.
It is not known if APTIOM is safe and effective in children under 4 years of age.

Who should not take APTIOM?
Do not take APTIOM if you are allergic to eslicarbazepine acetate, any of the other ingredients in APTIOM, or oxcarbazepine. See the end of this Medication Guide for a complete list of ingredients in APTIOM.

What should I tell my healthcare provider before taking APTIOM?
Before taking APTIOM, tell your healthcare provider about all your medical conditions, including if you:

- have or have had suicidal thoughts or actions, depression or mood problems
- have liver, kidney, or blood problems
- are allergic to oxcarbazepine. Some people who are allergic to oxcarbazepine may also be allergic to APTIOM.
- use birth control medicine. APTIOM may cause your birth control medicine to be less effective. Talk to your healthcare provider about the best birth control method to use.
- are pregnant or plan to become pregnant. APTIOM may harm your unborn baby. Tell your healthcare provider right away if you become pregnant while taking APTIOM. You and your healthcare provider will decide if you should take APTIOM while you are pregnant.
  - If you become pregnant while taking APTIOM, talk to your healthcare provider about registering with the North American Antiepileptic Drug (NAAED) Pregnancy Registry. The purpose of this registry is to collect information about the safety of antiepileptic medicine during pregnancy. You can enroll in this registry by calling 1-888-233-2334.
- are breastfeeding or plan to breastfeed. APTIOM passes into breast milk. You and your healthcare provider should discuss whether you should take APTIOM or breastfeed.

Tell your healthcare provider about all the medicines you take, including prescription and over-the-counter medicines, vitamins, and herbal supplements.
Taking APTIOM with certain other medicines may cause side effects or affect how well they work. Do not start or stop other medicines without talking to your healthcare provider.
Especially tell your healthcare provider if you take:

- oxcarbazepine
- phenobarbital

- carbamazepine
- phenytoin

- simvastatin
- birth control medicine

- omeprazole
- rosuvastatin

- clobazam
- primidone

Ask your healthcare provider or pharmacist for a list of these medicines, if you are not sure.
Know the medicines you take. Keep a list of them and show it to your healthcare provider and pharmacist when you get a new medicine.

How should I take APTIOM?

- Take APTIOM exactly as your healthcare provider tells you to take it.
- Do not stop taking APTIOM without talking to your healthcare provider. Stopping APTIOM suddenly can cause serious problems, including seizures that will not stop (status epilepticus).
- Your healthcare provider may change your dose.
- Your healthcare provider will tell you how much APTIOM to take.
- APTIOM can be taken with or without food.
- APTIOM can be taken as a whole tablet or crushed.
- If you take too much APTIOM, call your healthcare provider or go to the nearest hospital emergency room right away.
- Talk with your healthcare provider about what you should do if you miss a dose.

What should I avoid while taking APTIOM?

- Do not drive, operate heavy machinery, or do dangerous activities until you know how APTIOM affects you. APTIOM may slow your thinking and motor skills.

What are the possible side effects of APTIOM?
See “What is the most important information I should know about APTIOM?”
APTIOM may cause other serious side effects including:

- Nervous system problems. APTIOM may cause problems that can affect your nervous system. Symptoms of nervous system problems include:

- dizziness
- trouble concentrating

- trouble walking or with coordination
- vision problems

- feeling sleepy and tired

- Liver problems. APTIOM may affect your liver. Symptoms of liver problems include:

- yellowing of your skin or the whites of your eyes
- stomach pain

- nausea or vomiting
- dark urine

- loss of appetite

Get medical help right away if you have any of the symptoms listed above or listed in “What is the most important information I should know about APTIOM?”
The most common side effects of APTIOM include:

- dizziness
- vomiting

- sleepiness
- feeling tired

- nausea
- blurred vision

- headache
- shakiness

- double vision
- problems with coordination

Tell your healthcare provider if you have any side effect that bothers you or that does not go away.
These are not all the possible side effects of APTIOM. For more information, ask your healthcare provider or pharmacist.
Call your doctor for medical advice about side effects. You may report side effects to FDA at 1-800-FDA-1088.

How should I store APTIOM?

- Store APTIOM at 68oF to 77oF (20oC to 25oC).
- Safely throw away medicine that is out of date or no longer needed.

Keep APTIOM and all medicines out of reach of children.

What are the ingredients in APTIOM?
Active ingredient: eslicarbazepine acetate
Inactive ingredients: croscarmellose sodium, magnesium stearate, and povidone

General information about the safe and effective use of APTIOM.
Medicines are sometimes prescribed for purposes other than those listed in a Medication Guide. Do not use APTIOM for a condition for which it was not prescribed. Do not give APTIOM to other people, even if they have the same symptoms that you have. It may harm them.
This Medication Guide summarizes the most important information about APTIOM. If you would like more information, talk with your healthcare provider. You can ask your pharmacist or healthcare provider for information about APTIOM that is written for health professionals.
For more information, go to www.aptiom.com or call 1-888-394-7377.

Manufactured for: Sunovion Pharmaceuticals Inc., Marlborough, MA 01752 USA
Under license from
© 2023 Sunovion Pharmaceuticals Inc. All rights reserved.

This Medication Guide has been approved by the U.S. Food and Drug Administration.

Revised 9/2017

PACKAGE LABEL

PRINCIPAL DISPLAY PANEL – 200 MG 30 COUNT OBLONG BOTTLE

NDC 63402-202-30

30 Tablets

ONCE DAILY

Aptiom®

(eslicarbazepine acetate) Tablets

200 mg

Rx Only

ATTENTION DISPENSER: Each time Aptiom is
dispensed give the patient the accompanying
Medication Guide.

Sumitomo Pharma

Under license from Bial

PACKAGE LABEL

PRINCIPAL DISPLAY PANEL – 400 MG 30 COUNT OBLONG BOTTLE

NDC 63402-204-30

30 Tablets

ONCE DAILY

Aptiom®

(eslicarbazepine acetate) Tablets

400 mg

Rx Only

ATTENTION DISPENSER: Each time Aptiom is
dispensed give the patient the accompanying
Medication Guide.

Sumitomo Pharma

Under license from Bial

PACKAGE LABEL

PRINCIPAL DISPLAY PANEL – 600 MG 60 COUNT OBLONG BOTTLE

NDC 63402-206-60

60 Tablets

ONCE DAILY

Aptiom®

(eslicarbazepine acetate) Tablets

600 mg

Rx Only

ATTENTION DISPENSER: Each time Aptiom is
dispensed give the patient the accompanying
Medication Guide.

Sumitomo Pharma

Under license from Bial

PACKAGE LABEL

PRINCIPAL DISPLAY PANEL – 800 MG 30 COUNT OBLONG BOTTLE

NDC 63402-208-30

30 Tablets

ONCE DAILY

Aptiom®

(eslicarbazepine acetate) Tablets

800 mg

Rx Only

ATTENTION DISPENSER: Each time Aptiom is
dispensed give the patient the accompanying
Medication Guide.

Sumitomo Pharma

Under license from Bial

PACKAGE LABEL

PRINCIPAL DISPLAY PANEL – 200 MG SAMPLE WALLET

200 mg

per tablet

NDC 63402-202-07

ONCE DAILY

Aptiom®

(eslicarbazepine acetate) Tablets

200 mg

Rx Only

ATTENTION DISPENSER: Dispense the enclosed

Medication Guide to each patient.

This package contains 7 tablets.

Professional Sample

Not for Sale or Reimbursement

PACKAGE LABEL

PRINCIPAL DISPLAY PANEL – 400 MG SAMPLE WALLET

400 mg

per tablet

NDC 63402-204-07

ONCE DAILY

Aptiom®

(eslicarbazepine acetate) Tablets

400 mg

Rx Only

ATTENTION DISPENSER: Dispense the enclosed

Medication Guide to each patient.

This package contains 7 tablets.

Professional Sample

Not for Sale or Reimbursement

______________________________________________________________________________

PACKAGE LABEL

PRINCIPAL DISPLAY PANEL – 600 MG SAMPLE WALLET

600 mg

per tablet

NDC 63402-206-07

ONCE DAILY

Aptiom®

(eslicarbazepine acetate) Tablets

600 mg

Rx Only

ATTENTION DISPENSER: Dispense the enclosed

Medication Guide to each patient.

This package contains 7 tablets.

Professional Sample

Not for Sale or Reimbursement

______________________________________________________________________________

PACKAGE LABEL

PRINCIPAL DISPLAY PANEL – 800 MG SAMPLE WALLET

800 mg

per tablet

NDC 63402-208-07

ONCE DAILY

Aptiom®

(eslicarbazepine acetate) Tablets

800 mg

Rx Only

ATTENTION DISPENSER: Dispense the enclosed

Medication Guide to each patient.

This package contains 7 tablets.

Professional Sample

Not for Sale or Reimbursement

______________________________________________________________________________

PACKAGE LABEL

PRINCIPAL DISPLAY PANEL – TITRATION SAMPLE PACK WALLET

400 mg

per tablet and

800 mg

per tablet

Titration Sample Pack

NDC 63402-248-14

ONCE DAILY

Aptiom®

(eslicarbazepine acetate) Tablets

400 mg and 800 mg

Rx Only

ATTENTION DISPENSER: Dispense the enclosed

Medication Guide to each patient.

This package contains 14 tablets (7 tablets of 400 mg

and 7 tablets of 800 mg).

Professional Sample

Not for Sale or Reimbursement

PACKAGE LABEL

PRINCIPAL DISPLAY PANEL – 200 MG SAMPLE CARTON

NDC 63402-202-28

ONCE DAILY

Aptiom®

(eslicarbazepine acetate) Tablets

200 mg

ATTENTION DISPENSER: Dispense an enclosed

Medication Guide to each patient.

Rx Only

This package contains 28 tablets on 4 sample cards.

Each sample card contains 7 tablets each.

Please see the enclosed full Prescribing Information.

200 mg

per tablet

Professional Samples

Not for Sale or

Reimbursement

PACKAGE LABEL

PRINCIPAL DISPLAY PANEL – 400 MG SAMPLE CARTON

NDC 63402-204-28

ONCE DAILY

Aptiom®

(eslicarbazepine acetate) Tablets

400 mg

ATTENTION DISPENSER: Dispense an enclosed

Medication Guide to each patient.

Rx Only

This package contains 28 tablets on 4 sample cards.

Each sample card contains 7 tablets each.

Please see the enclosed full Prescribing Information.

400 mg

per tablet

Professional Samples

Not for Sale or

Reimbursement

______________________________________________________________________________

PACKAGE LABEL

PRINCIPAL DISPLAY PANEL – 600 MG SAMPLE CARTON

NDC 63402-206-28

ONCE DAILY

Aptiom®

(eslicarbazepine acetate) Tablets

600 mg

ATTENTION DISPENSER: Dispense an enclosed

Medication Guide to each patient.

Rx Only

This package contains 28 tablets on 4 sample cards.

Each sample card contains 7 tablets each.

Please see the enclosed full Prescribing Information.

600 mg

per tablet

Professional Samples

Not for Sale or

Reimbursement

______________________________________________________________________________

PACKAGE LABEL

PRINCIPAL DISPLAY PANEL – 800 MG SAMPLE CARTON

NDC 63402-208-28

ONCE DAILY

Aptiom®

(eslicarbazepine acetate) Tablets

800 mg

ATTENTION DISPENSER: Dispense an enclosed

Medication Guide to each patient.

Rx Only

This package contains 28 tablets on 4 sample cards.

Each sample card contains 7 tablets each.

Please see the enclosed full Prescribing Information.

800 mg

per tablet

Professional Samples

Not for Sale or

Reimbursement

______________________________________________________________________________

PACKAGE LABEL

PRINCIPAL DISPLAY PANEL – TITRATION SAMPLE PACK CARTON

NDC 63402-248-56

ONCE DAILY

Aptiom®

(eslicarbazepine acetate) Tablets

400 mg and 800 mg

ATTENTION DISPENSER: Dispense an enclosed

Medication Guide to each patient.

Rx Only

This package contains 56 tablets in 4 titration sample packs.

Each titration sample pack contains 14 tablets

(7 tablets of 400 mg and 7 tablets of 800 mg).

Please see the enclosed full Prescribing Information.

400 mg

per tablet and

800 mg

per tablet

Titration Sample Pack

Professional Samples

Not for Sale or

Reimbursement

______________________________________________________________________________